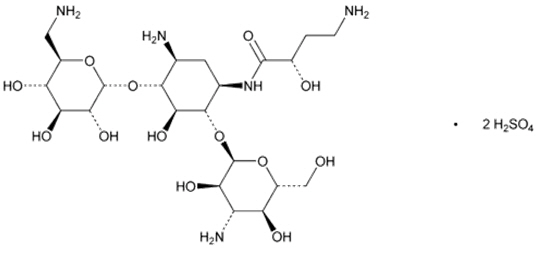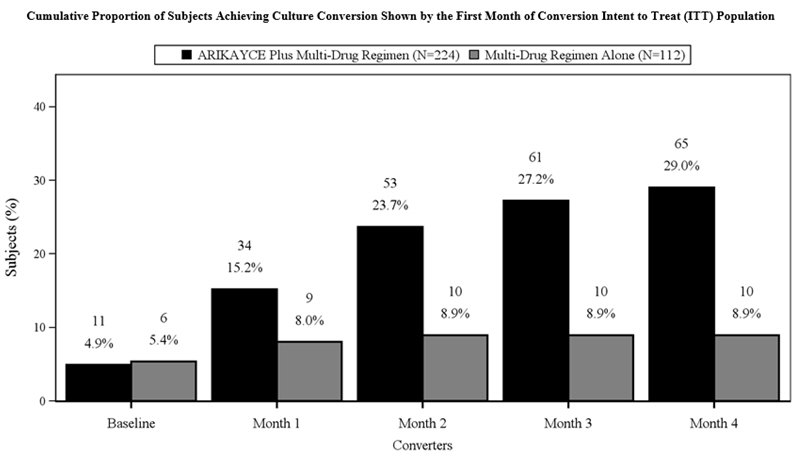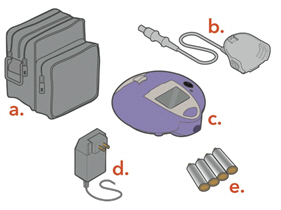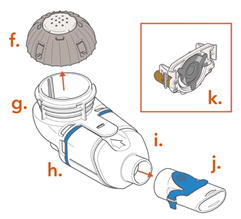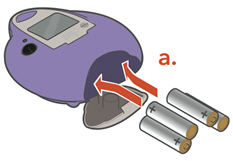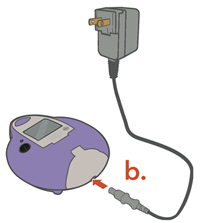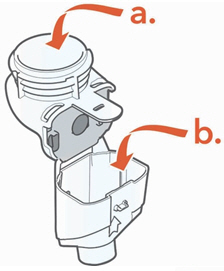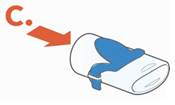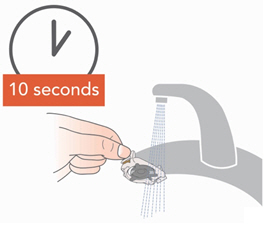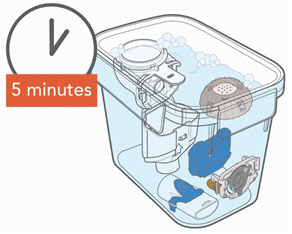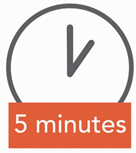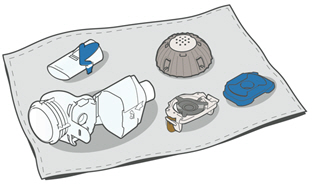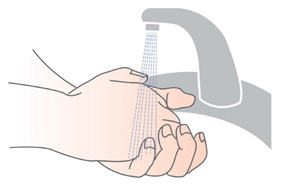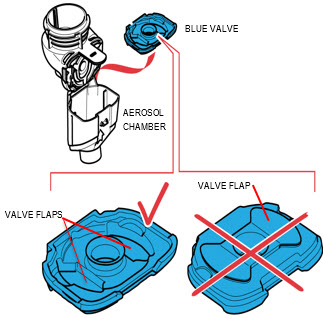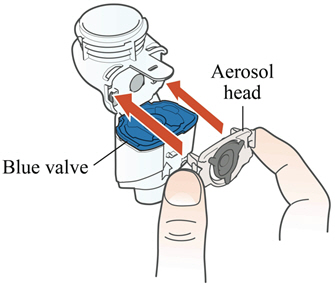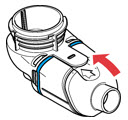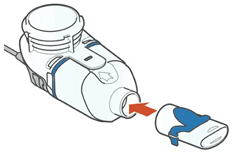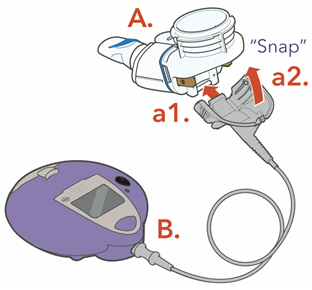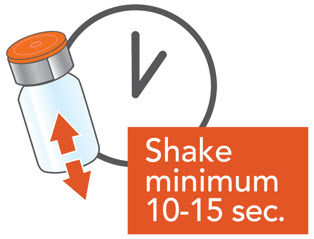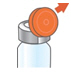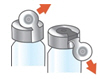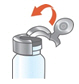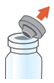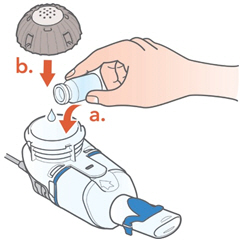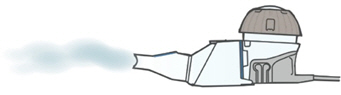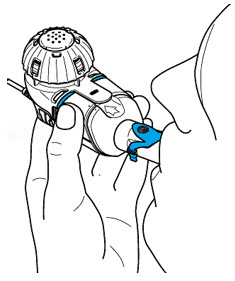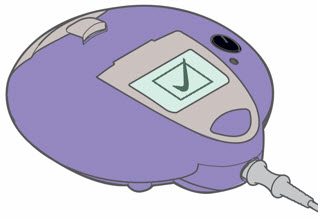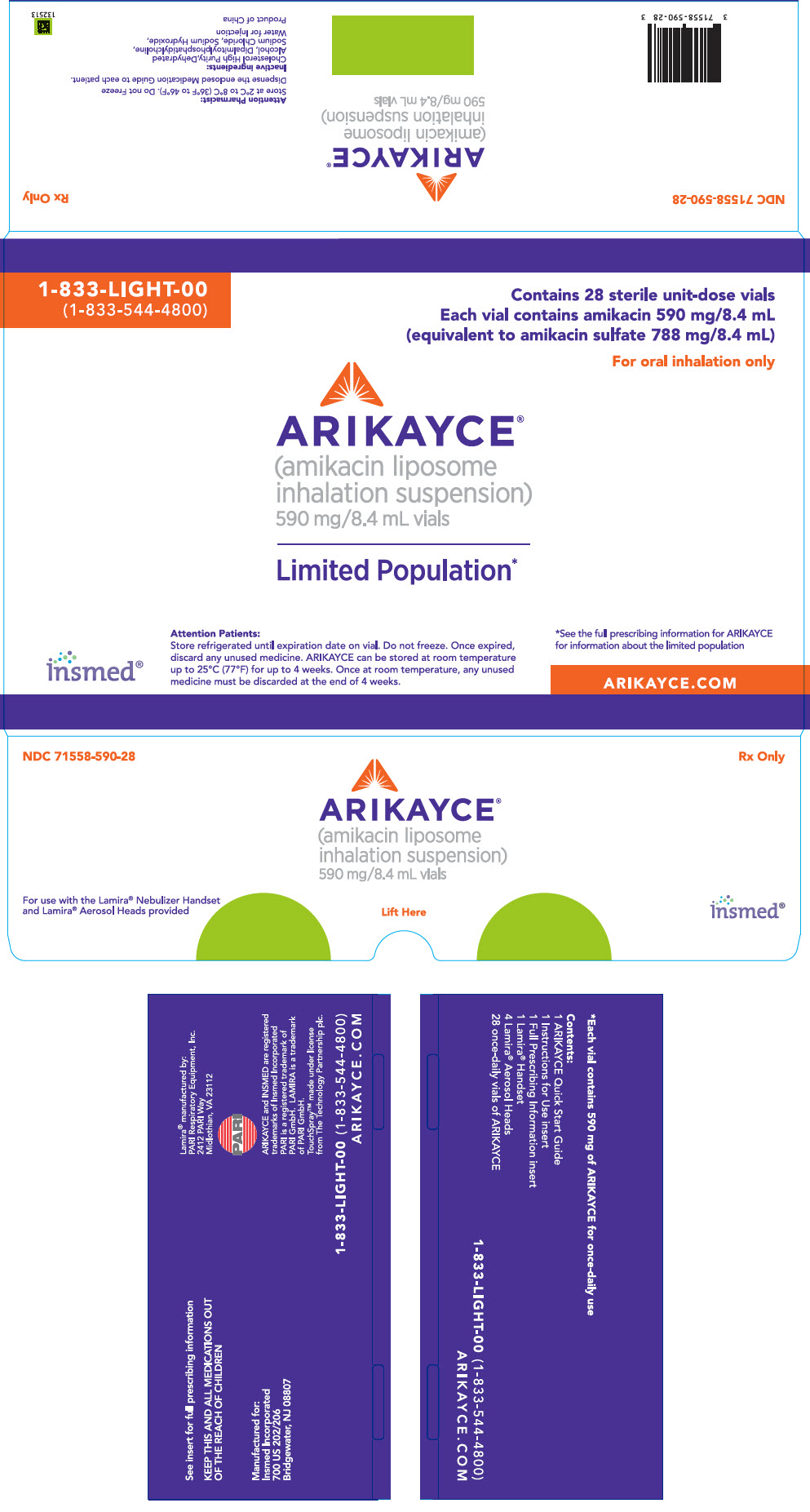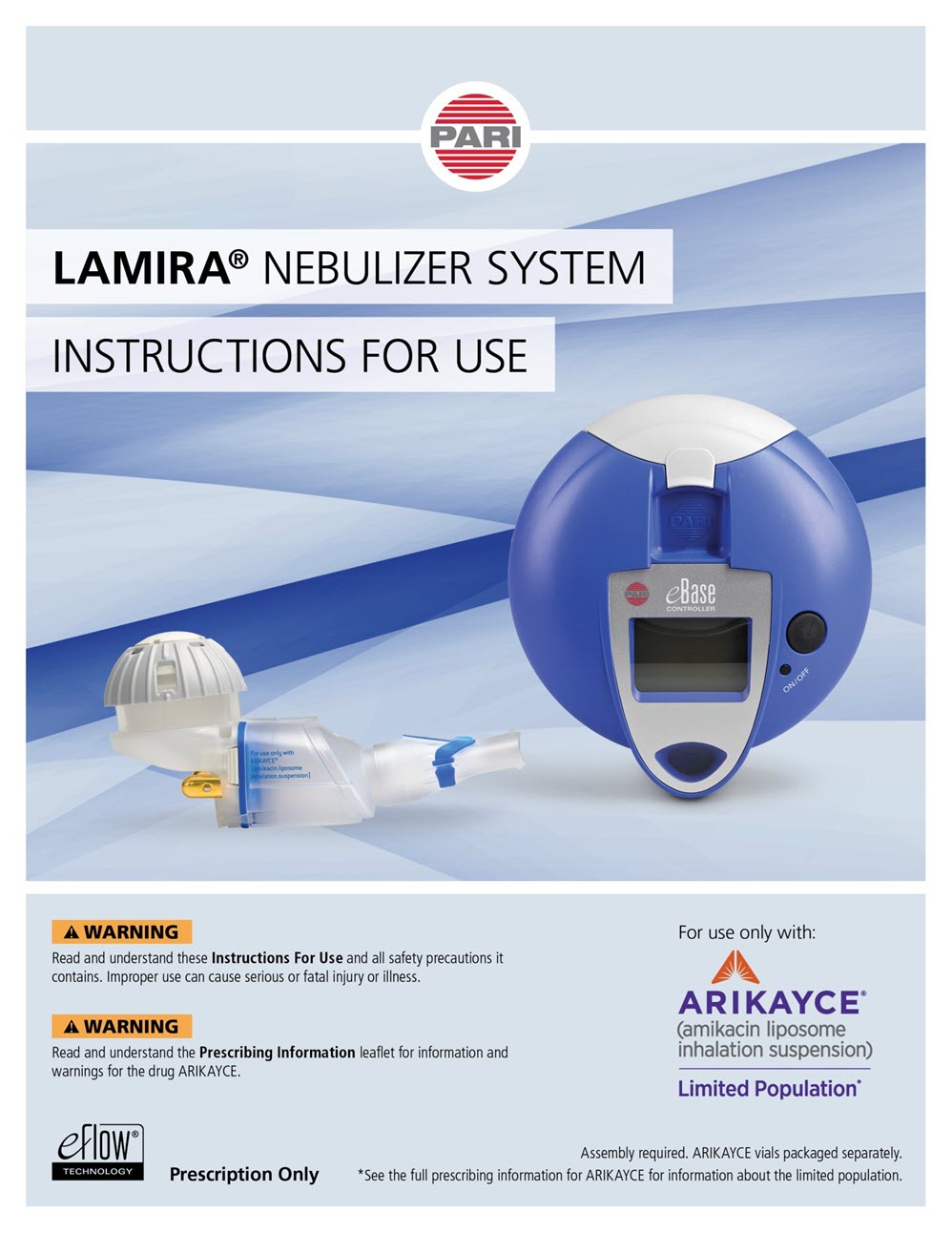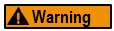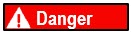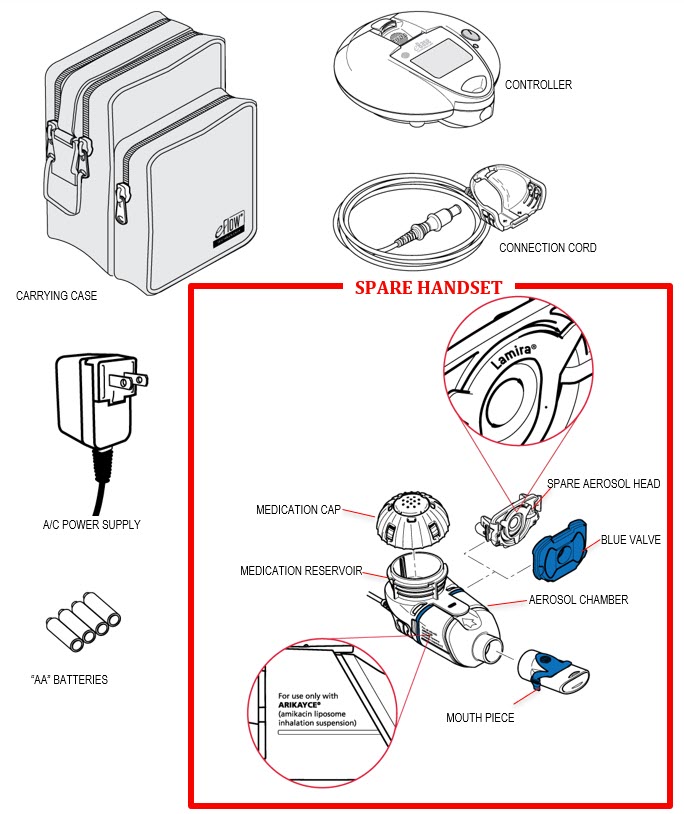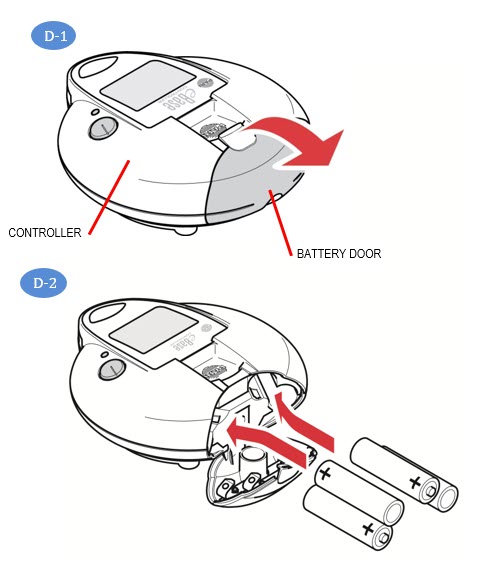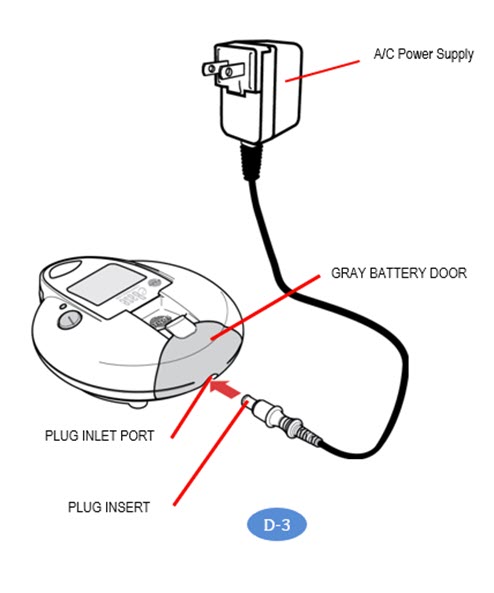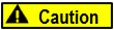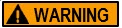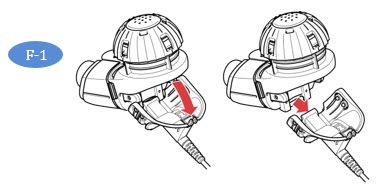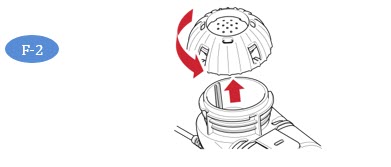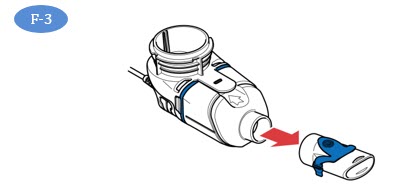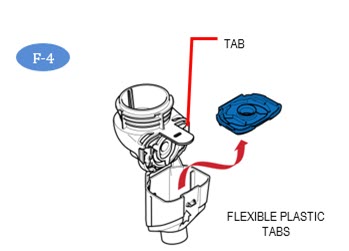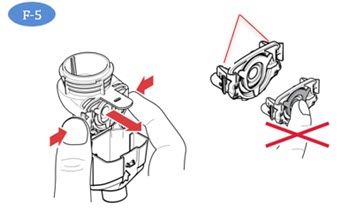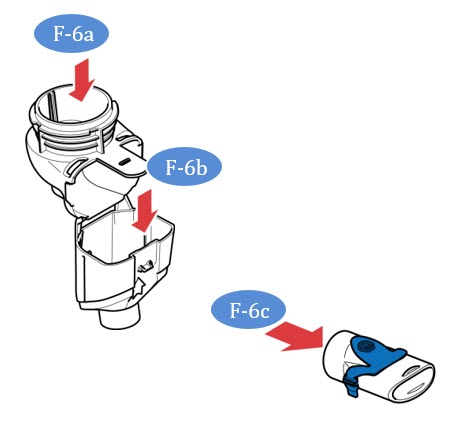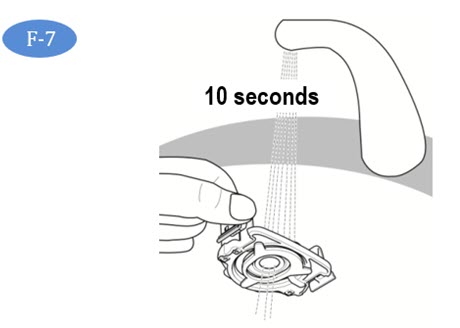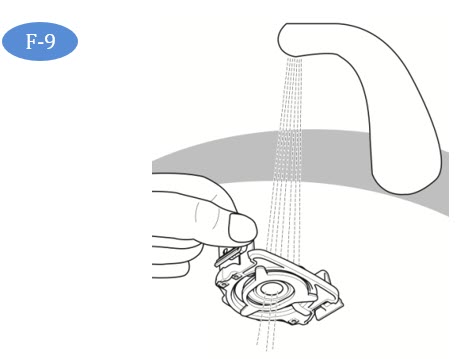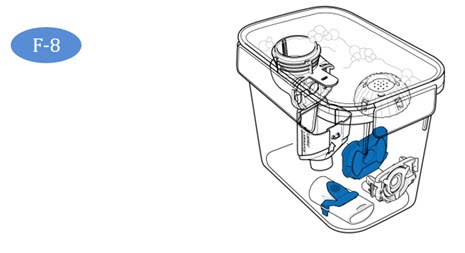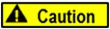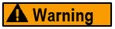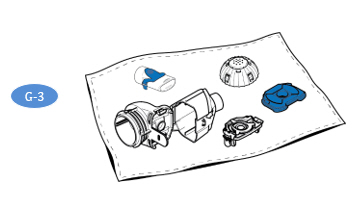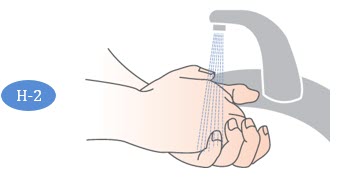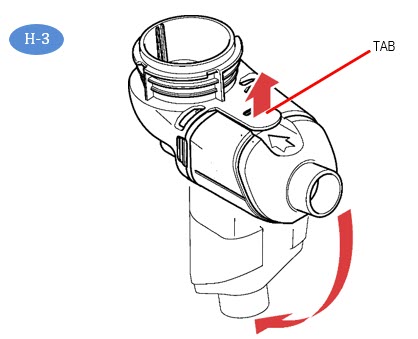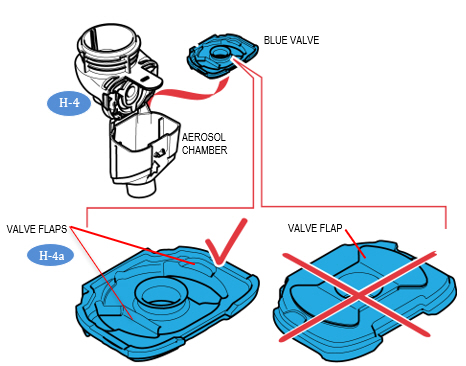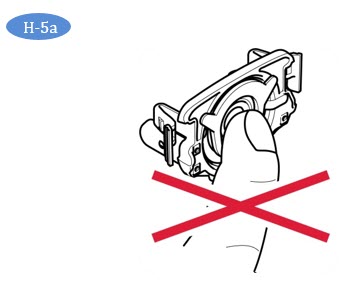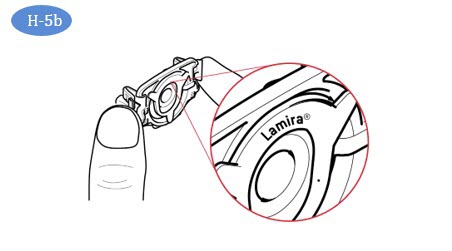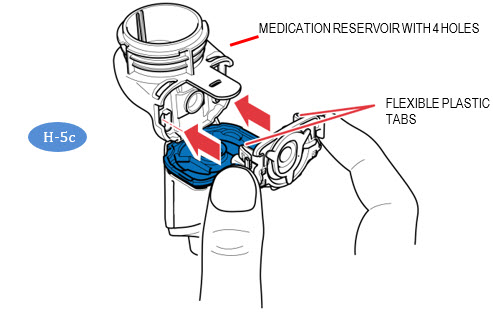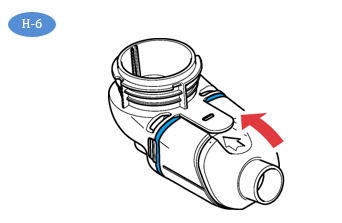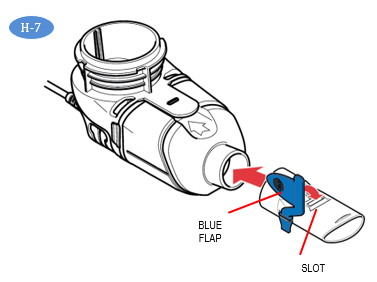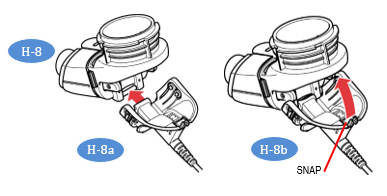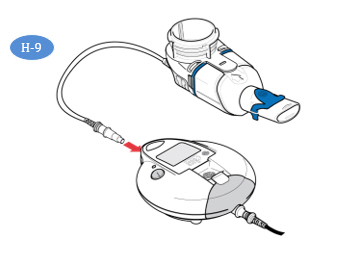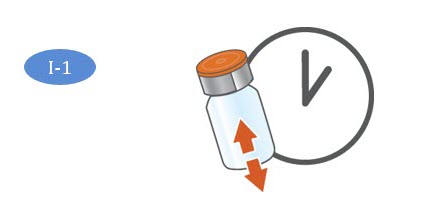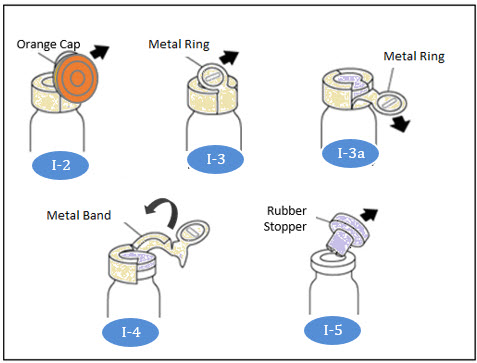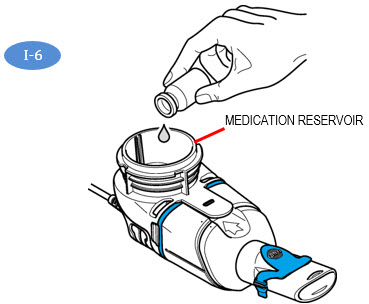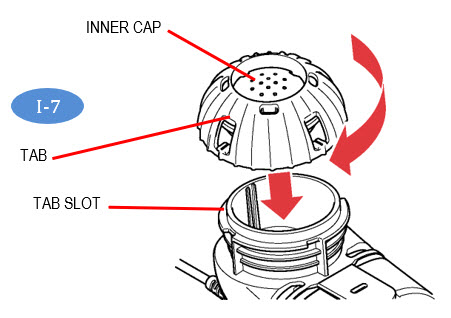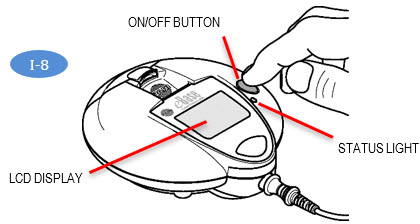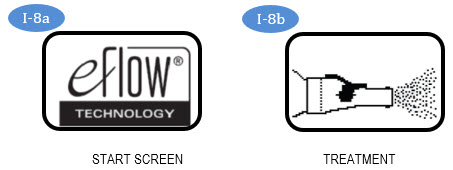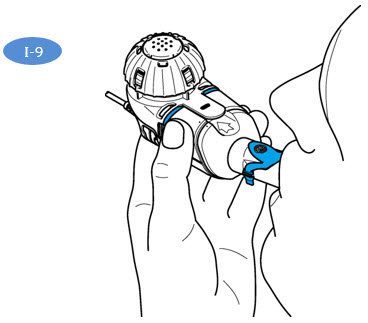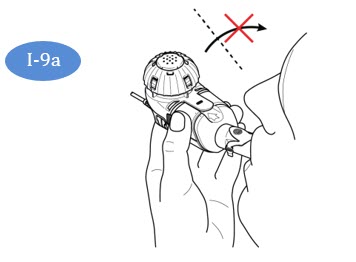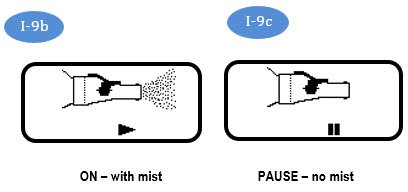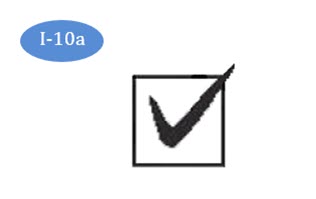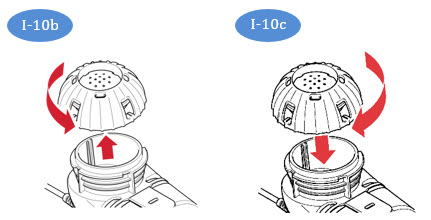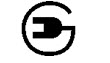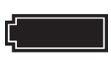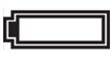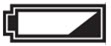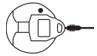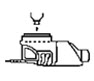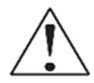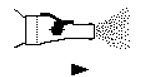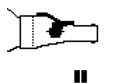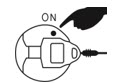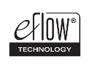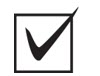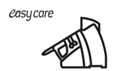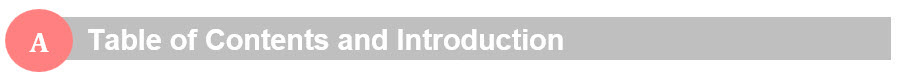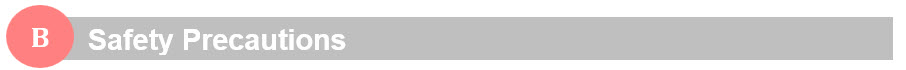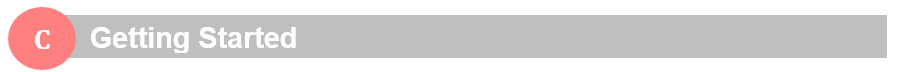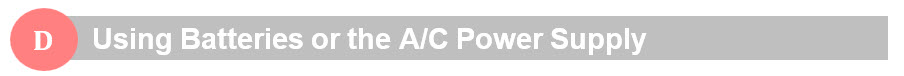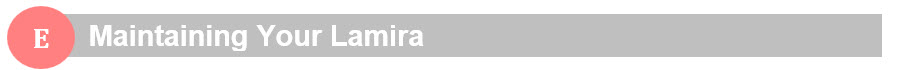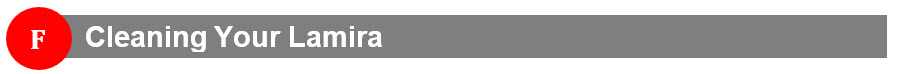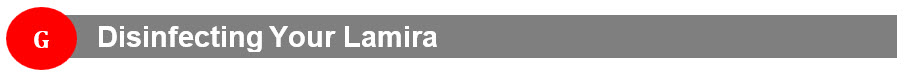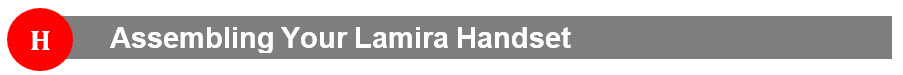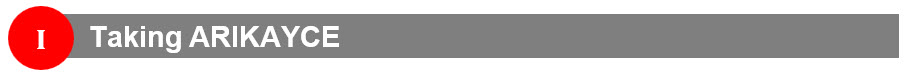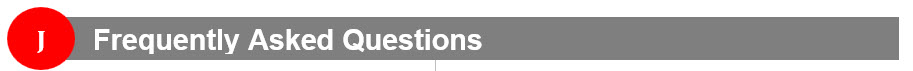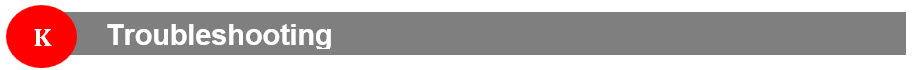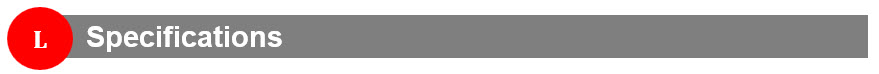 DRUG LABEL: ARIKAYCE
NDC: 71558-590 | Form: SUSPENSION
Manufacturer: Insmed Incorporated
Category: prescription | Type: HUMAN PRESCRIPTION DRUG LABEL
Date: 20251229

ACTIVE INGREDIENTS: Amikacin 590 mg/8.4 mL
INACTIVE INGREDIENTS: Cholesterol; DIPALMITOYLPHOSPHATIDYLCHOLINE, DL-; Sodium Chloride; Sodium Hydroxide; Water

HIGHLIGHTS OF PRESCRIBING INFORMATION

These highlights do not include all the information needed to use ARIKAYCE safely and effectively. See full prescribing information for ARIKAYCE.
ARIKAYCE® (amikacin liposome inhalation suspension), for oral inhalation use
Initial U.S. Approval: 2018
LIMITED POPULATION

WARNING: RISK OF INCREASED RESPIRATORY ADVERSE REACTIONS

See full prescribing information for complete boxed warning.

ARIKAYCE has been associated with a risk of increased respiratory adverse reactions, including, hypersensitivity pneumonitis, hemoptysis, bronchospasm, and exacerbation of underlying pulmonary disease that have led to hospitalizations in some cases. (5.1, 5.2, 5.3, 5.4)

1 INDICATIONS AND USAGE

LIMITED POPULATION: ARIKAYCE is an aminoglycoside antibacterial indicated in adults who have limited or no alternative treatment options, for the treatment of Mycobacterium avium complex (MAC) lung disease as part of a combination antibacterial drug regimen in patients who do not achieve negative sputum cultures after a minimum of 6 consecutive months of a multidrug background regimen therapy. As only limited clinical safety and effectiveness data for ARIKAYCE are currently available, reserve ARIKAYCE for use in adults who have limited or no alternative treatment options. This drug is indicated for use in a limited and specific population of patients. (1)

This indication is approved under accelerated approval based on achieving sputum culture conversion (defined as 3 consecutive negative monthly sputum cultures) by Month 6. Clinical benefit has not yet been established. (1)

Limitation of Use:

ARIKAYCE has only been studied in patients with refractory MAC lung disease defined as patients who did not achieve negative sputum cultures after a minimum of 6 consecutive months of a multidrug background regimen therapy. The use of ARIKAYCE is not recommended for patients with non-refractory MAC lung disease.

2 DOSAGE AND ADMINISTRATION

- For oral inhalation use only. (2.1)
- Use ARIKAYCE vials only with the Lamira Nebulizer System. (2.1)
- Pre-treatment with inhaled bronchodilator should be considered in patients with a history of hyperreactive airway disease. (2.1)
- The recommended dosage in adults is once daily oral inhalation of the contents of one 590 mg/8.4 mL ARIKAYCE vial. (2.2)

3 DOSAGE FORMS AND STRENGTHS

ARIKAYCE is supplied as a sterile, aqueous, liposome suspension for oral inhalation in a unit-dose glass vial containing amikacin 590 mg/8.4 mL. (3)

4 CONTRAINDICATIONS

ARIKAYCE is contraindicated in patients with a known hypersensitivity to any aminoglycoside. (4)

5 WARNINGS AND PRECAUTIONS

- Hypersensitivity Pneumonitis: Reported with ARIKAYCE treatment; if hypersensitivity pneumonitis occurs, discontinue ARIKAYCE and manage patients as medically appropriate. (5.1)
- Hemoptysis: Higher frequency of hemoptysis has been reported with ARIKAYCE treatment. If hemoptysis occurs, manage the patients as medically appropriate. (5.2)
- Bronchospasm: Higher frequency of bronchospasm has been reported with ARIKAYCE treatment. Treat patients as medically appropriate if this occurs during treatment with ARIKAYCE. (5.3)
- Exacerbations of Underlying Pulmonary Disease: Higher frequency of exacerbations of underlying pulmonary disease has been reported with ARIKAYCE treatment. Treat patients as medically appropriate if this occurs during treatment with ARIKAYCE. (5.4)
- Anaphylaxis and Hypersensitivity Reactions: Serious and potentially life-threatening hypersensitivity reactions, including anaphylaxis, have been reported in patients taking ARIKAYCE. If anaphylaxis or a hypersensitivity reaction occurs, discontinue ARIKAYCE and institute appropriate supportive measures. (5.5)
- Ototoxicity: Higher frequency of ototoxicity has been reported with ARIKAYCE treatment. Closely monitor patients with known or suspected auditory or vestibular dysfunction. If patients develop tinnitus this may be an early symptom of ototoxicity. (5.6)
- Nephrotoxicity: Nephrotoxicity was observed during the clinical trials of ARIKAYCE in patients with MAC lung disease but not at a higher frequency than the background regimen alone. Aminoglycosides have been associated with nephrotoxicity. Close monitoring of patients with known or suspected renal dysfunction may be needed when prescribing ARIKAYCE. (5.7)
- Neuromuscular Blockade: Aminoglycosides may aggravate muscle weakness by blocking the release of acetylcholine at neuromuscular junctions. Closely monitor patients with known or suspected neuromuscular disorders, such as myasthenia gravis. If neuromuscular blockade occurs, it may be reversed by the administration of calcium salts but mechanical respiratory assistance may be necessary. (5.8)
- Embryo-Fetal Toxicity: Aminoglycosides can cause fetal harm when administered to a pregnant woman. Aminoglycosides, including ARIKAYCE, may be associated with total, irreversible, bilateral congenital deafness in pediatric patients exposed in utero. Advise pregnant women of the potential risk to a fetus. (5.9, 8.1)

6 ADVERSE REACTIONS

Most common adverse reactions (incidence ≥10% and higher than control) in the patients with refractory MAC lung disease were: dysphonia, cough, bronchospasm, hemoptysis, musculoskeletal pain, upper airway irritation, ototoxicity, fatigue/asthenia, exacerbation of underlying pulmonary disease, diarrhea, nausea, and headache. (6.1)

To report SUSPECTED ADVERSE REACTIONS, contact Insmed Incorporated at 1-844-4-INSMED or FDA at 1-800-FDA-1088 or www.fda.gov/medwatch.

FULL PRESCRIBING INFORMATION

WARNING: RISK OF INCREASED RESPIRATORY ADVERSE REACTIONS

ARIKAYCE has been associated with an increased risk of respiratory adverse reactions including, hypersensitivity pneumonitis, hemoptysis, bronchospasm, exacerbation of underlying pulmonary disease that have led to hospitalizations in some cases [see Warnings and Precautions (5.1, 5.2, 5.3, 5.4)].

1 INDICATIONS AND USAGE

LIMITED POPULATION: ARIKAYCE® is indicated in adults, who have limited or no alternative treatment options, for the treatment of Mycobacterium avium complex (MAC) lung disease as part of a combination antibacterial drug regimen in patients who do not achieve negative sputum cultures after a minimum of 6 consecutive months of a multidrug background regimen therapy. As only limited clinical safety and effectiveness data for ARIKAYCE are currently available, reserve ARIKAYCE for use in adults who have limited or no alternative treatment options. This drug is indicated for use in a limited and specific population of patients.

This indication is approved under accelerated approval based on achieving sputum culture conversion (defined as 3 consecutive negative monthly sputum cultures) by Month 6. Clinical benefit has not yet been established [see Clinical Studies (14)]. Continued approval for this indication may be contingent upon verification and description of clinical benefit in confirmatory trials.

Limitation of Use:

ARIKAYCE has only been studied in patients with refractory MAC lung disease defined as patients who did not achieve negative sputum cultures after a minimum of 6 consecutive months of a multidrug background regimen therapy. The use of ARIKAYCE is not recommended for patients with non-refractory MAC lung disease.

2 DOSAGE AND ADMINISTRATION

2.1 Important Administration Instructions

ARIKAYCE is for oral inhalation use only. Administer by nebulization only with the Lamira® Nebulizer System. Refer to the Instructions for Use for full administration information on use of ARIKAYCE with the Lamira Nebulizer System.

Instruct patients using a bronchodilator ('reliever') to first use the bronchodilator following the bronchodilator leaflet for use information before using ARIKAYCE.

Pre-treatment with short-acting selective beta-2 agonists should be considered for patients with known hyperreactive airway disease, chronic obstructive pulmonary disease, asthma, or bronchospasm [see Warnings and Precautions (5.3)].

2.2 Recommended Dosage

The recommended dosage of ARIKAYCE in adults is once daily inhalation of the contents of one 590 mg/8.4 mL ARIKAYCE vial (590 mg of amikacin) using the Lamira Nebulizer System [see Clinical Studies (14)].

Administer ARIKAYCE with the Lamira Nebulizer System only. ARIKAYCE should be at room temperature before use. Prior to opening, shake the ARIKAYCE vial well for at least 10 to 15 seconds until the contents appear uniform and well mixed. The ARIKAYCE vial is opened by flipping up the plastic top of the vial then pulling downward to loosen the metal ring. The metal ring and the rubber stopper should be removed carefully. The contents of the ARIKAYCE vial can then be poured into the medication reservoir of the nebulizer handset.

If a daily dose of ARIKAYCE is missed, administer the next dose the next day. Do NOT double the dose to make up for the missed dose.

3 DOSAGE FORMS AND STRENGTHS

ARIKAYCE is supplied as a sterile, white, milky, aqueous, liposome suspension for oral inhalation in a unit-dose glass vial containing amikacin 590 mg/8.4 mL (equivalent to amikacin sulfate 788 mg/8.4 mL).

4 CONTRAINDICATIONS

ARIKAYCE is contraindicated in patients with a known hypersensitivity to any aminoglycoside.

5 WARNINGS AND PRECAUTIONS

5.1 Hypersensitivity Pneumonitis

Hypersensitivity pneumonitis has been reported with the use of ARIKAYCE in the clinical trials. Hypersensitivity pneumonitis (reported as allergic alveolitis, pneumonitis, interstitial lung disease, allergic reaction to ARIKAYCE) was reported at a higher frequency in patients treated with ARIKAYCE plus a background regimen (3.1%) compared to patients treated with a background regimen alone (0%). Most patients with hypersensitivity pneumonitis discontinued treatment with ARIKAYCE and received treatment with corticosteroids [see Adverse Reactions (6.1)].

If hypersensitivity pneumonitis occurs, discontinue ARIKAYCE and manage the patient as medically appropriate.

5.2 Hemoptysis

Hemoptysis has been reported with the use of ARIKAYCE in the clinical trials. Hemoptysis was reported at a higher frequency in patients treated with ARIKAYCE plus a background regimen (18.4%) compared to patients treated with a background regimen alone (13.4%) [see Adverse Reactions (6.1)]. If hemoptysis occurs, manage the patients as medically appropriate.

5.3 Bronchospasm

Bronchospasm has been reported with the use of ARIKAYCE in the clinical trials. Bronchospasm (reported as asthma, bronchial hyperreactivity, bronchospasm, dyspnea, dyspnea exertional, prolonged expiration, throat tightness, wheezing) was reported at a higher frequency in patients treated with ARIKAYCE plus a background regimen (28.7%) compared to patients treated with a background regimen alone (10.7%) [see Adverse Reactions (6.1)]. If bronchospasm occurs during the use of ARIKAYCE, treat the patients as medically appropriate.

5.4 Exacerbation of Underlying Pulmonary Disease

Exacerbations of underlying pulmonary disease have been reported with the use of ARIKAYCE in the clinical trials. Exacerbations of underlying pulmonary disease (reported as chronic obstructive pulmonary disease, infective exacerbation of chronic obstructive pulmonary disease, infective exacerbation of bronchiectasis) have been reported at a higher frequency in patients treated with ARIKAYCE plus a background regimen (15.2%) compared to patients treated with background regimen alone (9.8%) [see Adverse Reactions (6.1)]. If exacerbations of underlying pulmonary disease occur during the use of ARIKAYCE, treat the patients as medically appropriate.

5.5 Anaphylaxis and Hypersensitivity Reactions

Serious and potentially life-threatening hypersensitivity reactions, including anaphylaxis, have been reported in patients taking ARIKAYCE [see Adverse Reactions (6.1, 6.2)]. Signs and symptoms include acute onset of skin and mucosal tissue hypersensitivity reactions (hives, itching, flushing, swollen lips/tongue/uvula), respiratory difficulty (shortness of breath, wheezing, stridor, cough), gastrointestinal symptoms (nausea, vomiting, diarrhea, crampy abdominal pain), and cardiovascular signs and symptoms of anaphylaxis (tachycardia, low blood pressure, syncope, incontinence, dizziness). Before therapy with ARIKAYCE is instituted, evaluate for previous hypersensitivity reactions to aminoglycosides. If anaphylaxis or a hypersensitivity reaction occurs, discontinue ARIKAYCE and institute appropriate supportive measures.

5.6 Ototoxicity

Ototoxicity with use of ARIKAYCE

Ototoxicity has been reported with the use of ARIKAYCE in the clinical trials. Ototoxicity (including deafness, dizziness, presyncope, tinnitus, and vertigo) were reported with a higher frequency in patients treated with ARIKAYCE plus a background regimen (17%) compared to patients treated with background regimen alone (9.8%). This was primarily driven by tinnitus (8.1% in ARIKAYCE plus background regimen vs. 0.9% in the background regimen alone arm) and dizziness (6.3% in ARIKAYCE plus background regimen vs. 2.7% in the background regimen alone arm) [see Adverse Reactions (6.1)].

Closely monitor patients with known or suspected auditory or vestibular dysfunction during treatment with ARIKAYCE. If ototoxicity occurs, manage the patient as medically appropriate, including potentially discontinuing ARIKAYCE.

Risk of Ototoxicity Due to Mitochondrial DNA Variants

Cases of ototoxicity with aminoglycosides have been observed in patients with certain variants in the mitochondrially encoded 12S rRNA gene (MT-RNR1), particularly the m.1555A>G variant. Ototoxicity occurred in some patients even when their aminoglycoside serum levels were within the recommended range. Mitochondrial DNA variants are present in less than 1% of the general US population, and the proportion of the variant carriers who may develop ototoxicity as well as the severity of ototoxicity is unknown. In case of known maternal history of ototoxicity due to aminoglycoside use or a known mitochondrial DNA variant in the patient, consider alternative treatments other than aminoglycosides unless the increased risk of permanent hearing loss is outweighed by the severity of infection and lack of safe and effective alternative therapies.

5.7 Nephrotoxicity

Nephrotoxicity was observed during the clinical trials of ARIKAYCE in patients with MAC lung disease but not at a higher frequency than the background regimen alone [see Adverse Reactions (6.1)]. Nephrotoxicity has been associated with the aminoglycosides. Close monitoring of patients with known or suspected renal dysfunction may be needed when prescribing ARIKAYCE.

5.8 Neuromuscular Blockade

Patients with neuromuscular disorders were not enrolled in ARIKAYCE clinical trials. Aminoglycosides may aggravate muscle weakness by blocking the release of acetylcholine at neuromuscular junctions. Closely monitor patients with known or suspected neuromuscular disorders, such as myasthenia gravis. If neuromuscular blockade occurs, it may be reversed by the administration of calcium salts but mechanical respiratory assistance may be necessary.

5.9 Embryo-Fetal Toxicity

Aminoglycosides can cause fetal harm when administered to a pregnant woman. Aminoglycosides, including ARIKAYCE, may be associated with total, irreversible, bilateral congenital deafness in pediatric patients exposed in utero. Patients who use ARIKAYCE during pregnancy, or become pregnant while taking ARIKAYCE should be apprised of the potential hazard to the fetus [see Use in Specific Populations (8.1)].

6 ADVERSE REACTIONS

The following clinically significant adverse reactions are described in greater detail in other sections of labeling:

- Hypersensitivity pneumonitis [see Boxed Warning and Warnings and Precautions (5.1)]
- Hemoptysis [see Boxed Warning and Warnings and Precautions (5.2)]
- Bronchospasm [see Boxed Warning and Warnings and Precautions (5.3)]
- Exacerbation of Underlying Pulmonary Disease [see Boxed Warning and Warnings and Precautions (5.4)]
- Anaphylaxis and Hypersensitivity Reactions [see Warnings and Precautions (5.5)]
- Ototoxicity [see Warnings and Precautions (5.6)]
- Nephrotoxicity [see Warnings and Precautions (5.7)]
- Neuromuscular Blockade [see Warnings and Precautions (5.8)]

6.1 Clinical Trials Experience

Because clinical trials are conducted under widely varying conditions, adverse reaction rates observed in the clinical trials of a drug cannot be directly compared to rates in the clinical trials of another drug and may not reflect the rates observed in practice.

Overview of Clinical Trials for Safety Evaluation

Within the refractory NTM clinical program, 404 patients that participated in three clinical trials were treated with ARIKAYCE at the dose of 590 mg/day (median duration of exposure to ARIKAYCE was 236.5 days).

Trial 1 (NCT#02344004) was an open-label, randomized (2:1), multi-center Phase 3 trial in patients with refractory Mycobacterium avium complex (MAC) lung disease. Patients were randomized to either 8 months of ARIKAYCE plus a background regimen (n=223) or background regimen alone (n=112).

Trial 2 (NCT#02628600) was a single-arm extension of Trial 1 for refractory MAC lung disease patients that failed to achieve negative sputum cultures after 6 months of treatment or had a relapse or recurrence by Month 6 from either study arm of Trial 1. A total of 163 patients (n=90 from the prior background regimen alone arm of Trial 1, and n=73 from the prior ARIKAYCE plus background regimen arm in Trial 1) participated in the trial.

Trial 3 (NCT#01315236) was a double-blind, randomized, placebo-controlled Phase 2 study in patients with refractory nontuberculous mycobacterial (NTM) lung disease caused by MAC and Mycobacterium abscessus. Patients were randomized to either ARIKAYCE plus background regimen (N=44) or an inhaled diluted empty liposome placebo plus background regimen (N=45) for 84 days.

Across all clinical trials of patients with and without refractory NTM lung infection, 818 patients were exposed to multiple doses of ARIKAYCE.

Adverse Reactions Leading to Treatment Discontinuation

In the three NTM studies, there was a higher incidence of premature discontinuation of ARIKAYCE. In Trial 1, 34.5% discontinued ARIKAYCE prematurely; most were due to adverse reactions (18.8%) and withdrawal by subject (9.9%). In the comparator arm, 10.7% of subjects discontinued their background regimen, with 0.9% due to adverse reactions and 5.4% due to withdrawal by subject. In Trial 2 (the single-arm extension of Trial 1), 37.8% of patients starting on ARIKAYCE discontinued prematurely with 24.4% discontinuing due to adverse reactions. In Trial 3, all 9 (20.5%) premature discontinuations occurred in the ARIKAYCE plus background regimen-treated patients and there were no premature discontinuations in the placebo plus background regimen arm.

Serious Adverse Reactions in Trials 1 and 3

In Trial 1, 19.7% of patients treated with ARIKAYCE plus background regimen reported SAR as compared to 16.1% of patients treated with background regimen alone. In addition, in Trial 1 [2 to 1 randomization, ARIKAYCE plus background regimen versus background regimen alone], there were 80 hospitalizations in 41 patients (18.4%) treated with ARIKAYCE plus background regimen compared to 29 hospitalizations in 15 patients (13.4%) treated with background regimen alone. The most common SARs and reasons for hospitalization in the ARIKAYCE plus background regimen arm were related to exacerbation of underlying pulmonary disease and lower respiratory tract infections, such as pneumonia.

In Trial 3, 18.2% of patients treated with ARIKAYCE plus background regimen reported SARs compared to 8.9% of patients treated with background regimen plus inhaled placebo.

Common Adverse Reactions

The incidence of adverse reactions in Trial 1 are displayed in Table 1. Only those adverse reactions with a rate of at least 5% in the ARIKAYCE plus background regimen group and greater than the background regimen alone group, are shown.

Table 1: Adverse Reactions in ≥ 5% of ARIKAYCE-treated MAC Patients and More Frequent than Background Regimen Alone in Trial 1
Adverse Reaction | ARIKAYCE plus Background Regimen | Background Regimen Alone
 | (N=223) n (%) | (N=112) n (%)
Dysphonia [Includes aphonia and dysphonia] | 106 (48) | 2 (2)
Cough [Includes cough, productive cough, and upper airway cough syndrome] | 88 (40) | 19 (17)
Bronchospasm [Includes asthma, bronchial hyperreactivity, bronchospasm, dyspnea, dyspnea exertional, prolonged expiration, throat tightness, and wheezing] | 64 (29) | 12 (11)
Hemoptysis | 41 (18) | 15 (13)
Musculoskeletal pain [Includes back pain, arthralgia, myalgia, pain/body aches, muscle spasm and musculoskeletal pain] | 40 (18) | 10 (9)
Upper airway irritation [Includes oropharyngeal pain, oropharyngeal discomfort, throat irritation, pharyngeal erythema, upper airway inflammation, pharyngeal edema, vocal cord inflammation, laryngeal pain, laryngeal erythema, laryngitis] | 39 (18) | 2 (2)
Ototoxicity [Includes deafness, deafness neurosensory, deafness unilateral, dizziness, hypoacusis, presyncope, tinnitus, vertigo, balance disorders] | 38 (17) | 11 (10)
Fatigue and asthenia | 36 (16) | 11 (10)
Exacerbation of underlying pulmonary disease [Includes COPD, infective exacerbation of COPD, infective exacerbation of bronchiectasis] | 34 (15) | 11 (10)
Diarrhea | 28 (13) | 5 (5)
Nausea | 26 (12) | 4 (4)
Headache | 22 (10) | 5 (5)
Pneumonia [Includes atypical pneumonia, empyema, infection pleural effusion, lower respiratory tract infection, lung infection, lung infection pseudomonas, pneumonia, pneumonia aspiration, pneumonia pseudomonas, pseudomonas infection, and respiratory tract infection] | 20 (9) | 10 (9)
Pyrexia | 17 (8) | 5 (5)
Weight decreased | 16 (7) | 1 (1)
Vomiting [Includes vomiting and post-tussive vomiting] | 15 (7) | 4 (4)
Rash [Includes rash, rash maculo-papular, drug eruption, and urticaria] | 14 (6) | 1 (1)
Change in sputum [Includes increased sputum, sputum purulent, and sputum discolored] | 13 (6) | 1 (1)
Chest discomfort | 12 (5) | 3 (3)

Selected adverse drug reactions that occurred in <5% of patients and at higher frequency in ARIKAYCE-treated patients in Trial 1 are presented in Table 2.

Table 2: Selected Adverse Reactions in < 5% of ARIKAYCE-treated MAC Patients and More Frequent than Background Regimen Alone in Trial 1
Adverse Reaction | ARIKAYCE plus Background Regimen N=223 n (%) | Background Regimen Alone N=112 n (%)
Anxiety [Includes anxiety and anxiety disorder] | 10 (5) | 0 (0)
Oral fungal infection [Includes oral candidiasis and oral fungal infection] | 9 (4) | 2 (2)
Bronchitis | 8 (4) | 3 (3)
Dysgeusia | 7 (3) | 0 (0)
Hypersensitivity pneumonitis [Includes allergic alveolitis, interstitial lung disease, and pneumonitis] | 7 (3) | 0 (0)
Dry mouth | 6 (3) | 0 (0)
Epistaxis | 6 (3) | 1 (1)
Respiratory failure [Includes acute respiratory failure and respiratory failure] | 6 (3) | 2 (2)
Pneumothorax [Includes pneumothorax, pneumothorax spontaneous and pneumomediastinum] | 5 (2) | 1 (1)
Exercise tolerance decreased | 3 (1) | 0 (0)
Balance disorder | 3 (1) | 0 (0)
Neuromuscular disorder [Includes muscle weakness and neuropathy peripheral] | 2 (1) | 0 (0)

Refer to Table 1 and Table 2 for the incidence rate of hypersensitivity pneumonitis, bronchospasm, cough, dysphonia, exacerbation of underlying disease, hemoptysis, ototoxicity, upper airway irritation, and neuromuscular disorders [see Warnings and Precautions (5.1, 5.2, 5.3, 5.4, 5.6, 5.7)].

6.2 Postmarketing Experience

The following adverse reactions have been identified from postmarketing surveillance. Because these adverse reactions are reported voluntarily from a population of unknown size, precise estimates of frequency cannot be made and a causal relationship to drug exposure cannot be established.

Gastrointestinal disorders: dysphagia, glossitis, glossodynia, salivary hypersecretion, stomatitis, abdominal pain, abdominal distension

Immune system disorders: hypersensitivity, anaphylaxis, pharyngeal swelling [see Warnings and Precautions (5.5)]

Respiratory, thoracic, and mediastinal disorders: nasal dryness, rhinorrhea, sneezing, nasal congestion

7 DRUG INTERACTIONS

7.1 Drugs with Neurotoxic, Nephrotoxic, or Ototoxic Potential

Avoid concomitant use of ARIKAYCE with medications associated with neurotoxicity, nephrotoxicity, and ototoxicity.

7.2 Ethacrynic Acid, Furosemide, Urea, or Mannitol

Some diuretics can enhance aminoglycoside toxicity by altering aminoglycoside concentrations in serum and tissue. Avoid concomitant use of ARIKAYCE with ethacrynic acid, furosemide, urea, or intravenous mannitol.

8 USE IN SPECIFIC POPULATIONS

8.1 Pregnancy

Risk Summary

There are no data on ARIKAYCE use in pregnant women to evaluate for any drug-associated risk of major birth defects, miscarriage or adverse maternal or fetal outcomes. Although systemic absorption of amikacin following oral inhalation is expected to be low [see Clinical Pharmacology (12.3)], systemic exposure to aminoglycoside antibacterial drugs, including ARIKAYCE, may be associated with total, irreversible, bilateral congenital deafness when administered to pregnant women [see Warnings and Precautions (5.9)]. Advise pregnant women of the potential risk to a fetus.

Animal reproductive toxicology studies have not been conducted with inhaled amikacin. Subcutaneous administration of amikacin to pregnant rats (up to 100 mg/kg/day) and mice (up to 400 mg/kg/day) during organogenesis was not associated with fetal malformations. Ototoxicity was not adequately evaluated in offspring in animal studies.

The estimated background risk of major birth defects and miscarriage for the indicated populations is unknown. All pregnancies have a background risk of birth defect, loss, or other adverse outcomes. In the U.S. general population, the estimated background risk of major birth defects and miscarriage in clinically recognized pregnancies is 2-4% and 15-20%, respectively.

Data

Animal Data

No animal reproductive toxicology studies have been conducted with ARIKAYCE or non-liposomal amikacin administered by inhalation.

Amikacin was subcutaneously administered to pregnant rats (Gestation Days 8-14) and mice (Gestation Days 7-13) at doses of 25, 100, or 400 mg/kg to assess developmental toxicity. These doses did not cause fetal visceral or skeletal malformations in mice. The high dose was excessively maternally toxic in rats (nephrotoxicity and mortality were observed), precluding the evaluation of offspring at this dose. Fetal malformations were not observed at the low or mid dose in rats. Postnatal development of the rats and mice exposed to these doses of amikacin in utero did not differ significantly from control.

Ototoxicity was not adequately evaluated in offspring in animal developmental toxicology studies.

8.2 Lactation

Risk Summary

There is no information regarding the presence of ARIKAYCE in human milk, the effects on the breastfed infant, or the effects on milk production after administration of ARIKAYCE by inhalation. Although limited published data on other routes of administration of amikacin indicate that amikacin is present in human milk, systemic absorption of ARIKAYCE following inhaled administration is expected to be low [see Clinical Pharmacology (12.3)]. The developmental and health benefits of breastfeeding should be considered along with the mother's clinical need for ARIKAYCE and any potential adverse effects on the breastfed child from ARIKAYCE or from the underlying maternal condition.

8.4 Pediatric Use

Safety and effectiveness of ARIKAYCE in pediatric patients below 18 years of age have not been established.

8.5 Geriatric Use

In the NTM clinical trials, of the total number of patients receiving ARIKAYCE, 208 (51.5%) were ≥ 65 years and 59 (14.6%) were ≥ 75 years. No overall differences in safety and effectiveness were observed between elderly subjects and younger subjects. Because elderly patients are more likely to have decreased renal function, it may be useful to monitor renal function [see Warnings and Precautions (5.7)].

8.6 Hepatic Impairment

ARIKAYCE has not been studied in patients with hepatic impairment. No dose adjustments based on hepatic impairment are required since amikacin is not hepatically metabolized [see Clinical Pharmacology (12.3)].

8.7 Renal Impairment

ARIKAYCE has not been studied in patients with renal impairment. Given the low systemic exposure to amikacin following administration of ARIKAYCE, clinically relevant accumulation of amikacin is unlikely to occur in patients with renal impairment. However, renal function should be monitored in patients with known or suspected renal impairment, including elderly patients with potential age-related decreases in renal function [see Warnings and Precautions (5.7), Use in Specific Populations (8.5)].

10 OVERDOSAGE

Adverse reactions specifically associated with overdose of ARIKAYCE have not been identified. Acute toxicity should be treated with immediate withdrawal of ARIKAYCE, and baseline tests of renal function should be undertaken.

Hemodialysis may be helpful in removing amikacin from the body.

In all cases of suspected overdosage, physicians should contact the Regional Poison Control Center for information about effective treatment. In the case of any overdosage, the possibility of drug interactions with alterations in drug disposition should be considered.

11 DESCRIPTION

The active ingredient in ARIKAYCE (amikacin liposome inhalation suspension) is amikacin sulfate USP, an aminoglycoside antibacterial. Its chemical name is D-Streptamine, O-3-amino-3-deoxy-α-D-glucopyranosyl-(1→6)-O-[6-amino-6-deoxy-α-D-glucopyranosyl-(1→4)]-N^1-(4-amino-2-hydroxy-1-oxobutyl)-2-deoxy-, (S)-, sulfate (1:2) salt with a chemical formula of C22H43N5O13∙2H2SO4 with a molecular weight of 781.76. Its structural formula is:

ARIKAYCE is a white milky suspension consisting of amikacin sulfate encapsulated in liposomes and is supplied in a unit-dose 10 mL clear glass vial containing amikacin 590 mg/8.4 mL (equivalent to amikacin sulfate 788 mg/8.4 mL) as a sterile aqueous liposomal suspension for oral inhalation. ARIKAYCE consists of amikacin sulfate encapsulated in liposomes at a targeted concentration of 70 mg amikacin/mL with the pH range of 6.1 to 7.1 and lipid to amikacin weight ratio in the range of 0.60 to 0.79. The inactive ingredients are cholesterol, dipalmitoylphosphatidylcholine (DPPC), sodium chloride, sodium hydroxide (for pH adjustment), and water for injection.

ARIKAYCE is administered only using a Lamira Nebulizer System [see Dosage and Administration (2.1)]. Like all other nebulized treatments, the amount delivered to the lungs will depend upon patient factors. Under standardized in vitro testing per USP<1601> adult breathing pattern (500 mL tidal volume, 15 breaths per minute, and inhalation: exhalation ratio of 1:1), the mean delivered dose from the mouthpiece was approximately 312 mg of amikacin sulfate (53% of label claim). The mass median aerodynamic diameter (MMAD) of the nebulized aerosol droplets is about 4.7 µm (4.1 – 5.3 µm) as determined using the Next Generation Impactor (NGI) method. A percentage of the amikacin in the liposome is released by the nebulization process, thus nebulized ARIKAYCE delivers a combination of free and liposomal amikacin.

12 CLINICAL PHARMACOLOGY

12.1 Mechanism of Action

ARIKAYCE is an antibacterial drug [see Microbiology (12.4)].

12.2 Pharmacodynamics

ARIKAYCE exposure-response relationships and the time course of pharmacodynamic response are unknown.

12.3 Pharmacokinetics

Sputum Concentrations

Following once daily inhalation of 590 mg ARIKAYCE in Mycobacterium avium complex (MAC) patients, sputum concentrations at 1 to 4 hours post-inhalation were 1720, 884, and 1300 mcg/g at 1, 3, and 6 months, respectively. High variability in amikacin concentrations were observed (CV% >100%). After 48 to 72 hours post-inhalation, amikacin sputum concentrations decreased to approximately 5% of those at 1 to 4 hours post-inhalation.

Serum Concentrations

Following 3 months of once daily inhalation of 590 mg ARIKAYCE in MAC patients, the mean serum AUC0-24 was 23.5 mcg*hr/mL (range: 8.0 to 46.5 mcg*hr/mL; n=12) and the mean serum Cmax was 2.8 mcg/mL (range: 1.0 to 4.4 µg/mL; n=12). The maximum Cmax and AUC0-24 were below the mean Cmax of approximately 76 mcg/mL and AUC0-24 of 154 mcg*hr/mL observed for intravenous administration of amikacin sulfate for injection at the approved dosage of 15 mg/kg once daily in healthy adults.

Absorption

The bioavailability of ARIKAYCE is expected to vary primarily from individual differences in nebulizer efficiency and airway pathology.

Distribution

The protein binding of amikacin in serum is ≤ 10%.

Elimination

Following inhalation of ARIKAYCE in MAC patients, the apparent serum half-life of amikacin ranged from approximately 5.9 to 19.5 hrs.

Metabolism

Amikacin does not undergo appreciable metabolism.

Excretion

Systemically absorbed amikacin following ARIKAYCE administration is eliminated principally via glomerular filtration. On average, 7.42% (ranging from 0.72 to 22.60%; n=14) of the total ARIKAYCE dose was excreted in urine as unchanged drug compared to 94% following intravenous administration of amikacin sulfate for injection. Unabsorbed amikacin, following ARIKAYCE inhalation, is probably eliminated primarily by cellular turnover and expectoration.

Drug Interaction Studies

No clinical drug interaction studies have been conducted with ARIKAYCE [see Drug Interactions (7)].

12.4 Microbiology

Mechanism of Action

Amikacin is a polycationic, semisynthetic, bactericidal aminoglycoside. Amikacin enters the bacterial cell by binding to negatively charged components of the bacterial cell wall disrupting the overall architecture of the cell wall. The primary mechanism of action is the disruption and inhibition of protein synthesis in the target bacteria by binding to the 30S ribosomal subunit.

Resistance

The mechanism of resistance to amikacin in mycobacteria has been linked to mutations in the rrs gene of the 16S rRNA. In clinical trials, MAC isolates developing an amikacin MIC of > 64 mcg/mL after baseline were observed in a higher proportion of subjects treated with ARIKAYCE [see Clinical Studies (14)].

Interaction with Other Antimicrobials

There has been no in vitro signal for antagonism between amikacin and other antimicrobials against MAC based on fractional inhibitory concentration (FIC) and macrophage survival assays. In select instances, some degree of synergy between amikacin and other agents has been observed, as for example, synergy between aminoglycosides, including amikacin, and the beta-lactam class has been documented.

13 NONCLINICAL TOXICOLOGY

13.1 Carcinogenesis, Mutagenesis, Impairment of Fertility

In a 2-year inhalation carcinogenicity study, rats were exposed to ARIKAYCE for 15-25, 50-70, or 155-170 minutes per day for 96-104 weeks. These provided approximate inhaled doses of 5, 15, and 45 mg/kg/day. Squamous cell carcinoma was observed in the lungs of 2 of 120 rats administered the highest dose tested. Maximum serum AUC levels of amikacin in the rats at steady state were approximately 1.3, 2.8, and 7.6 mcg∙hr/mL at the low, mid, and high doses, respectively, compared with 23.5 mcg∙hr/mL (8.0 to 46.5 mcg∙hr/mL) measured in humans. The squamous cell carcinomas may be the result of a high lung burden of particulates from ARIKAYCE in the rat lung. The relevance of the lung tumor findings with regards to humans receiving ARIKAYCE is unknown.

No evidence of mutagenicity or genotoxicity was observed in a battery of in vitro and in vivo genotoxicity studies with a liposome-encapsulated amikacin formulation similar to ARIKAYCE (in vitro microbial mutagenesis test, in vitro mouse lymphoma mutation assay, in vitro chromosomal aberration study, and an in vivo micronucleus study in rats).

No fertility studies were conducted with ARIKAYCE. Intraperitoneal administration of amikacin to male and female rats at doses up to 200 mg/kg/day prior to mating through Day 7 of gestation were not associated with impairment of fertility or adverse effects on early embryonic development.

13.2 Animal Toxicology and/or Pharmacology

To provide information about chronic dosing of ARIKAYCE to another animal species, a 9-month inhalation toxicology study was conducted in dogs. Foamy alveolar macrophages associated with clearance of the inhaled product were present at dose-related incidence and severity, but they were not associated with inflammation, tissue hyperplasia, or the presence of preneoplastic or neoplastic changes. Dogs were exposed to ARIKAYCE for up to 90 minutes per day, providing inhaled amikacin doses of approximately 5, 10, and 30 mg/kg/day.

14 CLINICAL STUDIES

Trial 1 (NCT#02344004) was an open-label, randomized (2:1), multi-center trial in patients with refractory Mycobacterium avium complex (MAC) lung disease as confirmed by at least 2 sputum culture results. Patients were considered to have refractory MAC lung disease if they did not achieve negative sputum cultures after a minimum duration of 6 consecutive months of background regimen therapy that was either ongoing or stopped no more than 12 months before the screening visit. Patients were randomized to either ARIKAYCE plus a background regimen or background regimen alone. The surrogate endpoint for assessing efficacy was based on achieving culture conversion (3 consecutive monthly negative sputum cultures) by Month 6. The date of conversion was defined as the date of the first of the 3 negative monthly cultures, which had to be achieved by Month 4 in order to meet the endpoint by Month 6. Patients who achieved culture conversion by Month 6 were continued on study drug (ARIKAYCE plus background regimen or background regimen alone based on their randomization) for a total of 12 months after the first negative sputum culture.

A total of 336 patients were randomized (ARIKAYCE plus background regimen, n=224; background regimen alone, n=112) (ITT population), with a mean age of 64.7 years and there was a higher percentage of females (69.3%) than males (30.7%) in the study. At the time of enrollment, of the 336 subjects in the ITT population, 302 (89.9%) were either on a guideline-based regimen for MAC or off guideline-based therapy for MAC for less than 3 months while 34 (10.1%) were off treatment for 3 to 12 months prior to enrollment. At screening, patients were stratified by smoking status (current smoker or not) and by whether patients were on treatment or off treatment for at least 3 months. Most patients at screening were not current smokers (89.3%) and had underlying bronchiectasis (62.5%). At baseline, 329 patients were on a multidrug background regimen that included a macrolide (93.3%), a rifamycin (86.3%), or ethambutol (81.4%). Overall, 55.6% of subjects were receiving a triple-drug background regimen consisting of a macrolide, a rifamycin and ethambutol.

The proportion of patients achieving culture conversion (3 consecutive monthly negative sputum cultures) by Month 6 was significantly (p<0.0001) greater for ARIKAYCE plus background regimen (65/224, 29.0%) compared to background regimen alone (10/112, 8.9%). Of those receiving ARIKAYCE plus background regimen, 18.3% (41/224) achieved culture conversion by Month 6 and sustained sputum culture conversion (defined as consecutive negative sputum cultures with no positive culture on solid media or no more than 2 consecutive positive cultures on liquid media following culture conversion) for up to 12 months of treatment after the first culture that defined culture conversion, compared to 2.7% (3/112) of patients receiving background regimen alone (p<0.0001). At 3 months after the completion of treatment, 16.1% (36/224) of patients who had received ARIKAYCE plus background regimen maintained durable culture conversion, compared to 0% of patients who had received background regimen alone (p<0.0001).

In Trial 1, 23/224 (10.3%) of patients had MAC isolates that developed MIC of > 64 mcg/mL while receiving treatment with ARIKAYCE. In the background regimen alone arm, 4/112 (3.6%) of patients had MAC isolates that developed amikacin MIC of > 64 mcg/mL.

Additional endpoints to assess the clinical benefit of ARIKAYCE, for example, change from baseline in six-minute walk test distance and the Saint George's Respiratory Questionnaire, did not demonstrate clinical benefit by Month 6.

16 HOW SUPPLIED/STORAGE AND HANDLING

16.1 How Supplied

ARIKAYCE (amikacin liposome inhalation suspension), 590 mg/8.4 mL, is supplied in a sterile, unit-dose 10-mL glass vial. The product is dispensed as a 28-vial kit.

Each carton contains a 28-day supply of medication (28 vials). In addition to the ARIKAYCE vials in the carton, one Lamira Nebulizer Handset and four Lamira Aerosol Heads are provided.

NDC 71558-590-28

The Lamira Nebulizer System contains a controller, a spare Aerosol Head, a spare Handset, Power Cord and accessories.

16.2 Storage and Handling

Store ARIKAYCE vials refrigerated at 2°C to 8°C (36°F to 46°F) until expiration date on vial. Do not freeze. Once expired, discard any unused drug.

ARIKAYCE can be stored at room temperature up to 25°C (77°F) for up to 4 weeks. Once at room temperature, any unused drug must be discarded at the end of 4 weeks.

17 PATIENT COUNSELING INFORMATION

Advise the patient to read the FDA-approved patient labeling (Medication Guide and Patient Instructions for Use).

Important Instructions for Administration of ARIKAYCE

Instruct patients to read the Instructions for Use before starting ARIKAYCE. Instruct patients to only use the Lamira® Nebulizer System to administer ARIKAYCE. Advise the patient or caregiver not to use the Lamira Nebulizer System with any other medicine.

Hypersensitivity Pneumonitis and Bronchospasm (Difficulty Breathing)

Advise patients to inform their healthcare provider if they experience shortness of breath or wheezing after administration of ARIKAYCE. Advise patients with a history of reactive airway disease, asthma, or bronchospasm, to administer ARIKAYCE after using a short-acting bronchodilator [see Warnings and Precautions (5.1, 5.3)].

Hemoptysis or Cough

Advise patients to inform their healthcare provider if they cough up blood or experience episodic cough either during or after ARIKAYCE administration particularly in the first month after starting ARIKAYCE [see Warnings and Precautions (5.2) and Adverse Reactions (6.1)].

Exacerbations of Underlying Pulmonary Disease

Advise patients to inform their healthcare provider if they experience worsening of their lung disease after starting ARIKAYCE [see Warnings and Precautions (5.4)].

Dysphonia or Difficulty Speaking

Advise patients to inform their healthcare provider if they have difficulty speaking. Difficulty speaking or loss of ability to speak has been reported with ARIKAYCE [see Adverse Reactions (6.1)].

Anaphylaxis and Hypersensitivity Reactions

Advise patients and caregivers that serious and potentially life-threatening hypersensitivity reactions, that require immediate treatment could occur. Advise the patient to discontinue ARIKAYCE and seek immediate medical attention if any signs or symptoms of a hypersensitivity reaction occur [see Warnings and Precautions (5.5)].

Ototoxicity (Ringing in the Ears)

Advise patients to inform their healthcare provider if they experience ringing in the ears, dizziness, or any changes in hearing because ARIKAYCE has been associated with hearing loss [see Warnings and Precautions (5.6)].

Advise the patient not to operate heavy machinery or do dangerous activities while inhaling ARIKAYCE through the Lamira Nebulizer System because ARIKAYCE can cause symptoms such as dizziness or respiratory symptoms.

Nephrotoxicity or Kidney Damage

Advise patients to inform their health care provider if they have kidney problems because kidney damage has been reported with aminoglycosides [see Warnings and Precautions (5.7)].

Neuromuscular Blockade

Advise patients to inform their healthcare provider of known neuromuscular disease (e.g., myasthenia gravis) [see Warnings and Precautions (5.8)].

Embryo-Fetal Toxicity

Advise pregnant women that aminoglycosides, including ARIKAYCE, may cause irreversible congenital deafness when administered during pregnancy [see Warnings and Precautions (5.9) and Use in Special Populations (8.1)].

Manufactured for:

Insmed Incorporated
Bridgewater, NJ 08807

Insmed® and ARIKAYCE® are trademarks of Insmed Incorporated. Lamira® is a trademark of PARI Pharma GmbH.

© 2018 Insmed Incorporated. All rights reserved.

For patent information: www.insmed.com/program-patents

MEDICATION GUIDE
ARIKAYCE (ar' i kase) LIMITED POPULATION
(amikacin liposome inhalation suspension)
for oral inhalation use

Important: For oral inhalation only.

What is the most important information I should know about ARIKAYCE?

ARIKAYCE can cause serious side effects, including:

- allergic inflammation of the lungs: These respiratory problems may be symptoms of allergic inflammation of the lungs and often come with:

- fever
- coughing
- fast breathing

- wheezing
- shortness of breath

- coughing up of blood (hemoptysis): Coughing up blood is a serious and common side effect of ARIKAYCE.
- severe breathing problems: Severe breathing problems can be symptoms of bronchospasm. Bronchospasm is a serious and common side effect of ARIKAYCE. Bronchospasm symptoms include:

- shortness of breath
- wheezing

- difficult or labored breathing
- coughing or chest tightness

- worsening of chronic obstructive pulmonary disease (COPD): This is a serious and common side effect of ARIKAYCE.

- serious allergic reactions: Serious allergic reactions that may lead to death have happened to people who take ARIKAYCE. Stop taking ARIKAYCE right away and get emergency medical help if you have any of the following symptoms of a serious allergic reaction:

- hives
- itching
- redness or blushing of the skin (flushing)
- swollen lips, tongue or throat
- trouble breathing or wheezing
- shortness of breath

- noisy high-pitched breathing (stridor)
- cough
- nausea
- vomiting
- diarrhea
- feel cramps in your stomach area

- fast heart rate
- feeling light headed
- feeling faint
- loss of control of the bowels or bladder (incontinence)
- dizziness

While using ARIKAYCE these side effects may become serious enough that treatment in a hospital is needed.

Call your healthcare provider or get medical help right away if you have any of these serious side effects while taking ARIKAYCE. Your healthcare provider may ask you to stop using ARIKAYCE for a short period of time or completely stop using ARIKAYCE.

What is ARIKAYCE?

ARIKAYCE is a prescription medicine used to treat adults with refractory (difficult to treat) Mycobacterium avium complex (MAC) lung disease as part of a combination antibacterial drug treatment plan (regimen).

It is not known if ARIKAYCE is safe and effective in children younger than 18 years of age.

This product was approved by FDA using the Limited Population pathway. This means FDA has approved this drug for a limited and specific patient population, and studies on the drug may have only answered focused questions about its safety and effectiveness.

Do not use ARIKAYCE if you:

- are allergic to any aminoglycoside, or any of the ingredients in ARIKAYCE. See "What are the ingredients in ARIKAYCE?" at the end of this leaflet for a complete list of ingredients in ARIKAYCE.

Before using ARIKAYCE, tell your healthcare provider about all of your medical conditions, including if you:

- have asthma, chronic obstructive pulmonary disease (COPD), shortness of breath or wheezing (bronchospasm).
- have been told you have poor lung function.
- have or have had hearing problems (including noises in your ears such as ringing or hissing), hearing loss, or your mother has had hearing problems after taking an aminoglycoside.
- have been told you have certain gene variants (a change in the gene) related to hearing abnormalities inherited from your mother.
- have dizziness or sense of the room spinning.
- have kidney problems.
- have neuromuscular disease such as myasthenia gravis.
- are pregnant or plan to become pregnant. It is not known if ARIKAYCE can harm your unborn baby. ARIKAYCE is in a class of medicines that may be connected with complete deafness in babies at birth. The deafness affects both ears and cannot be changed.
- are breastfeeding or plan to breastfeed. It is not known if the medicine in ARIKAYCE passes into your breast milk and if it can harm your baby. Talk to your healthcare provider about the best way to feed your baby during treatment with ARIKAYCE.

Tell your healthcare provider about all the medicines you take, including prescription medicines and over-the-counter medicines, vitamins, and herbal supplements.

How should I use ARIKAYCE?

- Read the step-by-step instructions for using ARIKAYCE at the end of the Medication Guide and the full Instructions for Use provided in your kit. The manufacturer's Instructions for Use provides complete information about how to put together (assemble), prepare, use, clean, and disinfect your Lamira® Nebulizer System.
- Do not use ARIKAYCE unless you understand the directions provided. If you have questions talk to your health care provider or call Insmed inLighten™ Patient Support at 1-833-LIGHT-00 (1-833-544-4800).
- Use ARIKAYCE exactly as your healthcare provider tells you to use it. Do not use ARIKAYCE more often than prescribed for you.
- Only use ARIKAYCE with the Lamira Nebulizer System.
- Inhale each daily dose of ARIKAYCE 1 time each day through the Lamira Nebulizer Handset. Do not use more than 1 vial of ARIKAYCE in a day.
- Do not use ARIKAYCE after the expiration date on the vial. If you forget to take your daily dose of ARIKAYCE, take your next dose at your usual time the next day.
- Do not double the dose to make up for the missed dose.
- Do not stop using ARIKAYCE or other medicines to treat your MAC lung disease unless told to do so by your healthcare provider.
- If you use too much ARIKAYCE, call your healthcare provider or go to the nearest emergency room right away.

What are the possible side effects of ARIKAYCE?

ARIKAYCE may cause serious side effects, including:

- See "What is the most important information I should know about ARIKAYCE?"
- hearing loss or ringing in the ears (ototoxicity). Ototoxicity is a serious and common side effect of ARIKAYCE. Tell your healthcare provider right away if you have hearing loss or you hear noises in your ears such as ringing or hissing. Tell your healthcare provider if you start having problems with balance or dizziness (vertigo).
- worsening kidney problems (nephrotoxicity). ARIKAYCE is in a class of medicines which may cause worsening kidney problems. Your healthcare provider may do a blood test to check how well your kidneys are working during your treatment with ARIKAYCE.
- worsening muscle weakness (neuromuscular blockade). ARIKAYCE is in a class of medicines which can cause muscle weakness to get worse in people who already have problems with muscle weakness (myasthenia gravis).

The most common side effects of ARIKAYCE include:

- changes in your voice and hoarseness (dysphonia)
- tiredness (fatigue)
- headache
- rash
- cough during or after a dose of ARIKAYCE, especially in the first month after starting treatment.

- sore throat
- diarrhea
- fever
- decreased weight
- chest discomfort

- muscle pain
- nausea
- vomiting
- increased sputum

These are not all of the possible side effects of ARIKAYCE.

Call your doctor or pharmacist for medical advice about side effects. You may report side effects to FDA at 1-800-FDA-1088.

How should I store ARIKAYCE?

- Store ARIKAYCE vials refrigerated between 36°F to 46°F (2°C to 8°C) until the expiration date on the vial. Do not freeze.
- After ARIKAYCE has been stored in the refrigerator, any unused medicine must be thrown away (disposed of) after the expiration date on the vial.
- Store ARIKAYCE vials at room temperature between 68°F to 77°F (20°C to 25°C) for up to 4 weeks.
- After ARIKAYCE has been stored at room temperature any unused medicine must be thrown away (disposed of) at the end of 4 weeks.
- Use an opened ARIKAYCE vial right away.
- Throw away the ARIKAYCE vial right away after use.

Keep ARIKAYCE and all medicines out of the reach of children.

General information about safe and effective use of ARIKAYCE

Medicines are sometimes prescribed for purposes other than those listed in a Medication Guide. Do not use ARIKAYCE for a condition for which it was not prescribed. Do not give ARIKAYCE to other people even if they have the same symptoms that you have. It may harm them. You can ask your pharmacist or healthcare provider for information about ARIKAYCE that is written for health professionals.

What are the ingredients in ARIKAYCE?

Active ingredient: amikacin sulfate

Inactive ingredients: Dipalmitoylphosphatidylcholine (DPPC), cholesterol, sodium chloride, sodium hydroxide (for pH adjustment), and water for injection

Manufactured for: Insmed Incorporated, 700 US Highway 202/206, Bridgewater, NJ 08807-1704

© 2018 Insmed Incorporated. All rights reserved. Insmed®, ARIKAYCE®, and inLighten™ are trademarks of Insmed Incorporated. Lamira® is a trademark of PARI Pharma GmbH.

For more information, call Insmed inLighten Patient Support at: 1- 833-LIGHT-00 (1-833-544-4800)

This Medication Guide has been approved by the U.S. Food and Drug Administration

Issued: 12/2025

Instructions for Use

ARIKAYCE® LIMITED POPULATION
(amikacin liposome inhalation suspension)

For oral inhalation use
Lamira® Nebulizer System

Before using your Lamira Nebulizer System, be sure you read and understand the detailed information in the full Instructions for Use that comes with the Lamira Nebulizer System. This will provide more complete information about how to put together (assemble), prepare, use, clean, and disinfect your Lamira Nebulizer System. If you do not understand any part of the instructions, contact Insmed inLighten™ Patient Support at 1-833-LIGHT-00 (1-833-544-4800) before using the Lamira Nebulizer System.

Gather your ARIKAYCE medicine. The ARIKAYCE 28-day kit contains:

- 1 ARIKAYCE Quick Start Guide
- 1 Instructions for Use insert
- 1 Full Prescribing Information insert
- 1 Lamira Nebulizer Handset
- 4 Lamira Aerosol Heads (1 in each weekly box)
- 28 vials (1 vial each day) of ARIKAYCE (7 in each weekly box)

Check to make sure you have all the necessary parts for your Lamira Nebulizer System:

a. Carrying Case
b. Connection Cord
c. Controller
d. A/C Power Supply
e. "AA" Batteries

Spare Lamira Nebulizer Handset:

f. Medication Cap and Seal
g. Medication Reservoir
h. Blue Valve
i. Aerosol Chamber
j. Mouthpiece
k. Spare Aerosol Head

You will also need the following supplies that do not come in your ARIKAYCE 28-day kit that will help you care for your Lamira Nebulizer System:

- Clear liquid soap for cleaning the Handset and Aerosol Head
- Distilled water for disinfecting the Handset and Aerosol Head

Choose your power supply and get it ready.

a. 4 "AA" batteries

or

b. A/C Power Supply
  - Plug the A/C Power Supply into the Controller.
  - Plug the A/C Power Supply into the wall outlet.

Do not insert the A/C Power into the front of the Controller.

Cleaning and Disinfecting

Before first use, rinse, clean, and disinfect your Handset and Aerosol Head. Moving forward, rinse, clean, and disinfect the Handset including the Aerosol Head after every use.

When you receive your Handset and Aerosol Head, they will not be sterile. Cleaning and disinfecting your Handset and Aerosol Head is important to reduce the risk of infection, illness, and contamination.

1. Cleaning the Handset and Aerosol Head Reminder: Before first use, rinse and clean the Handset and Aerosol Head. Moving forward, rinse and clean the Handset including the Aerosol Head right after each use.

- Take apart (disassemble) the Handset for cleaning
- Gently wipe away any drops of medicine from the Medication Reservoir (a), Aerosol Chamber (b), and Mouthpiece (c) before rinsing, to reduce antibiotics added to water systems.
  Use only plain, dry paper towels or wipes. Do not use towels or wipes that have any chemicals added to them such as alcohol, lotion, or baby wipes.

Be careful not to harm the parts. Do not wipe Aerosol Head.
Throw away paper towels by disposing in trash with solid waste.

- Rinse each of the parts under warm running tap water for 10 seconds. Rinse the Aerosol Head for 10 seconds on each side.

- Clean all Handset parts by adding a few drops of clear liquid dish soap and warm tap water to a clean tub or bowl. Cover the Handset parts in the warm soapy water and soak for 5 minutes, shaking them periodically. Then rinse them thoroughly under warm running tap water.

2. Disinfecting the Handset and Aerosol Head Before First Use Reminder: Disinfect the Handset and Aerosol Head before first use.

- Be sure your Handset and Aerosol Head are clean before you disinfect.
- Make sure the pot has enough distilled water to completely cover all the Handset parts, including the Aerosol Head.
- Heat the water to a boil in a clean pot.
- Place the Handset parts, including the Aerosol Head, into the boiling water.
- Boil for a full 5 minutes. Note: It may be helpful to use a timer.

- Air dry on a lint-free towel. When fully dry, wrap up the parts in a lint-free towel for storage. You can put them together again just before taking your next treatment.

Assembling Your Handset

Step 1: Wash your hands with soap and water, and dry them well.

Step 2: Insert the Blue Valve.
Open the Handset by gently pulling up on the tab of the Medication Reservoir.
Insert the Blue Valve so that it rests on top of the Aerosol Chamber with the 2 valve flaps facing down (valve flaps not bent).

Step 3: Insert the Aerosol Head.

Grasp the Aerosol Head by the 2 flexible plastic tabs on each side. Be sure the text "Lamira®" is facing toward you and is at the top of the Aerosol Head.
Squeeze the 2 flexible plastic tabs together while inserting the Aerosol Head into the Medication Reservoir.
Close the Handset when you are done (no gaps along blue valve edge).
Do not touch the silver part of the Aerosol Head at any time.
After the Aerosol Head has been used 7 times, throw away (dispose of) and replace with a new one during the cleaning process. Lamira Handset is to be used for 28 days.

Step 4: Attach the Mouthpiece to your Handset with the Blue Flap facing up.

Step 5: Finally, attach the Handset to the Controller.

a. Attach the Connection Cord to the Handset.
  a1. Line up the bottom of the Connector with the bottom of the Handset.
  a2. Push upward against the Handset until you hear the pieces snap together.

b. Connect the Connection Cord to the Controller.

Taking ARIKAYCE

Your ARIKAYCE should be at room temperature before use to make sure that your Lamira Nebulizer System operates properly. Do not use other medicines in your Handset.

Bring ARIKAYCE to room temperature by removing it from the refrigerator at least 45 minutes before use. Do not use if your ARIKAYCE has been frozen.

Step 1: Get your ARIKAYCE ready.

- Place the Handset on a clean, flat, stable surface.
- Shake the ARIKAYCE vial for a minimum of 10 to 15 seconds, AND UNTIL THE MEDICINE LOOKS THE SAME THROUGHOUT AND WELL MIXED.

How to open the ARIKAYCE vial

- Lift the orange cap from the vial.

- Grip the metal ring on top of the vial and pull it down gently until 1 side breaks away from the vial but do not pull the tab completely off.

- Pull the metal band from around the vial top in a circular motion until it comes off completely.

- Carefully remove the rubber stopper.

1. Open the vial and pour the ARIKAYCE into the Medication Reservoir.
2. Attach the Medication Cap.

Step 2: Sit in a relaxed, upright position.

- Press and hold down on the On/Off button for a few seconds to turn the Lamira on.
- Mist will begin to flow.

Step 3: Insert the Mouthpiece (but do not cover the blue flap) and take slow, deep breaths.

- Then, breathe normally in and out through the Mouthpiece until your treatment is complete.
- Treatment should take about 14 minutes but could take up to 20 minutes.

Be sure to hold the Handset level throughout the treatment.

Step 4: Check that your treatment has ended.

- The Lamira will beep 2 times.
- A Checkmark will briefly appear on the screen.
- The Controller will automatically shut off.
- Remove the Medication Cap and check the Medication Reservoir to make sure that no more than a few drops of ARIKAYCE remains. If ARIKAYCE remains, replace the Medication Cap, press the On/Off button, and complete your dose.

For any issues you may have with your Lamira Nebulizer System, see Section J – Frequently Asked Questions and Section K – Troubleshooting of the full Instructions for Use that comes with your medicine.

Cleaning your Lamira Handset and Aerosol Head After Use

- Rinse, clean, and disinfect handset right away after each use to reduce infection, illness, and contamination.
- Disinfect the Handset and Aerosol Head after every use.
- See "Cleaning and Disinfecting" at the beginning of the Instructions for Use on how to properly clean and disinfect your handset and aerosol head.

© 2018 Insmed Incorporated. All rights reserved. Insmed®, ARIKAYCE®, and inLighten™ are trademarks of Insmed Incorporated. Lamira® is a trademark of PARI Pharma GmbH.

This Instructions for Use has been approved by the U.S. Food and Drug Administration.
Issued: 01/2025

INSTRUCTIONS FOR USE

Table of Contents
A. Introduction | 1
B. Safety Precautions | 2
C. Getting Started | 3
D. Using Batteries or the A/C Power Supply | 4
E. Maintaining Your Lamira | 5
F. Cleaning Your Lamira | 6
G. Disinfecting Your Lamira | 9
H. Assembling Your Lamira Handset | 10
I. Taking ARIKAYCE | 13
J. Frequently Asked Questions | 16
K. Troubleshooting | 17
L. Specifications | 19

Introduction

The Lamira® Nebulizer System (Lamira) is a battery operated electronic nebulizer, which vibrates and forces liquid ARIKAYCE® (amikacin liposome inhalation suspension) through thousands of small holes to form an aerosol mist for inhalation.

These Instructions for Use contain information and safety precautions for the Lamira nebulizer that is made just for the medicine ARIKAYCE. Do not use any other medicine in the Lamira nebulizer.

Before using your Lamira nebulizer, read and understand all the Instructions for Use and save them for future reference. If you do not understand any part of these directions, contact the Insmed® inLighten™ Patient Support Program at 1-833-LIGHT-00 (1-833-544-4800) before using the Lamira nebulizer.

To reduce the risk of infection, illness, or injury from contamination or improper use, it is important to complete the following 2 steps:

1) Before first use, rinse and clean the Handset including the Aerosol Head. Moving forward, rinse and clean the Handset including the Aerosol Head right after each use (see Section F). Do not wash the Controller, Connection Cord, or A/C Power Supply. Use clear liquid soap made for washing dishes to clean the Handset including the Aerosol Head. Do not use liquid dish soaps that are white or antibacterial liquid dish soaps because these may contain additives harmful to the Aerosol Head.
2) Before first use, disinfect the Handset including the Aerosol Head. Moving forward, disinfect the Handset including the Aerosol Head after every use (see Section G).

Take special note of all safety precautions marked Danger and Warning.

Indications for use

Limited by Federal Law for use only with ARIKAYCE.

Read all dangers and warnings before using.

To reduce the risk of fatal injury from electrocution:

- Do not place or store the Lamira Nebulizer System near water or other liquid such as bathtub or sink. Do not place or drop into water or other liquid. Do not use while bathing.
- Do not reach for the Lamira Nebulizer System if it has fallen into water or other liquid. Unplug right away. Pick up the Lamira only after it has been unplugged.

To reduce the risk of serious injury:

- The Lamira Nebulizer Handset (Handset) is for single patient use. Do not share your Handset with other people.
- The Handset is made just for ARIKAYCE. Never use other medicine in the Handset. Using other medicine in the Lamira nebulizer can result in severe injury or death.
- Read, understand and follow all warnings and instructions in these Instructions for Use before using the Lamira nebulizer.
- To reduce the risk of fire, burns and damage or malfunction of the Controller:
  ✓ Do not overload wall outlets or use extension cords.
  ✓ Keep all electrical cords away from heated surfaces.
  ✓ Do not spray liquids onto the housing of the Controller (Controller). (See Section C: Getting Started) Liquid may cause damage to the electrical parts and could lead to a malfunction. If liquids enter the Controller, contact the inLighten Patient Support Program at 1-833-LIGHT-00 (1-833-544-4800).
  ✓ Do not insert any object into any opening on the Lamira.
  ✓ Do not operate where oxygen is being given in a closed environment such as an oxygen tent.
- Always unplug the Lamira right after using and before cleaning.
- Before use, check your Lamira for proper assembly. All parts must be connected and firmly in place. Use of an improperly assembled Lamira could decrease or stop the effectiveness of your treatment.
- Use only A/C power supply and accessories that are made for the Lamira. Use of unapproved A/C power supply or accessories can lead to improper administration, injury, leading to damage to the Controller.
- Never substitute the Handset for any other eFlow® Technology Handset such as Altera®, eRapid® or any other eFlow®. Never use the Lamira Aerosol Head (Aerosol Head) in any other eFlow® Technology Handset. This Aerosol Head has unique performance characteristics for ARIKAYCE.
- Never operate the Controller if it is improperly or incompletely assembled or damaged. See Section K: Troubleshooting for more information about alerts that appear when the Lamira is improperly assembled or might be damaged.
- Never operate the Lamira if:
  ✓ It has damaged cords or plugs,
  ✓ it is not working properly,
  ✓ it has been dropped or damaged,
  ✓ the Controller has been exposed to liquids
- To reduce the risk of infection, illness, or injury from contamination, clean and dry all parts of the Handset after each use. Follow the instructions in Section E to maintain and clean the Lamira.
- Cleaning the Handset properly will help prevent the Aerosol Head from clogging. Replace the Aerosol Head with a new one after 7 uses. Lamira Handset is to be used for 28 days. If the Aerosol Head becomes clogged, the aerosol mist will be reduced, which may increase your inhalation time of therapy. If clogging occurs, use the instructions in Section F to clean the Aerosol Head.
- Cleaning the Handset and Aerosol Head only removes the medicine and saliva. To reduce the risk of serious or fatal illness caused by contamination of the Handset, you must also disinfect the Handset and Aerosol Head after every cleaning. See Section G for disinfection instructions.
- The Lamira contains small parts that may become a choking hazard to small children. The Lamira Connection Cord (Connection Cord) also may become a strangulation hazard.
- Do not allow pets, for example dogs or rodents, near the cables.
- Keep the Lamira out of reach of children.
- Keep the Handset level when in use. Excessive tilting can cause the Controller to shut off leaving unused ARIKAYCE in the Medication Reservoir and resulting in incomplete dosing.
- Closely supervise use when the Lamira is used near children or the physically or mentally impaired.
- Do not use your Lamira while driving or in any situation which takes away your full attention.
- If the Lamira has been damaged or is not operating properly, contact the inLighten Patient Support Program at 1-833-LIGHT-00 (1-833-544-4800).
- Do not take the Controller apart at any time. There are no user serviceable parts inside the Controller. Contact the inLighten Patient Support Program at 1-833-LIGHT-00 (1-833-544-4800) for all Controller service needs.
- Do not modify this equipment without authorization from the manufacturer.
- Do not use the device in areas exposed to elevated electromagnetic or electrical radiation such as a MRI scanner or high frequency surgical equipment.
- Do not place near other medical devices during operation unless both devices are monitored constantly to make sure both are operating properly.
- Do not use within 12 inches (30 cm) of portable wireless communication devices such as cell phones or antenna cables or external antennas.
- Do not use near airplane or train control systems. Do not use aboard aircraft.
- Do not use the nebulizer near anti-theft systems and Radio Frequency Identification (RFID) readers, which are used in a wide variety of settings, including stores, libraries, and hospitals. Do not power on the nebulizer when passing through security screening or theft protection (RFID) systems at entrances or exits of stores, libraries or hospitals. Note that some entrance and exit security systems are not visible.

Technical electromagnetic compatibility data is available in table form upon request from PARI Pharma GmbH or on the internet at https://www.pari.com/fileadmin/Electromagnetic-compatibility-4.pdf

Step C1:

Gather your dosing supplies:

- Clear liquid soap for cleaning the Handset
- Distilled water for disinfecting the Handset
- The ARIKAYCE 28-day drug kit will contain the following:
  - 28 vials of ARIKAYCE (1 vial to be used each day for 28 days)
  - 4 Lamira Aerosol Heads (1 Aerosol Head to be used for 7 days and then replaced)
  - 1 Lamira Handset (to be used for 28 days until the next ARIKAYCE drug box arrives)
  - 1 ARIKAYCE Quick Start Guide
  - 1 Instructions For Use Insert
  - 1 Full Prescribing Information Insert

Step C2:

Check your Lamira Nebulizer System package to make sure you have the items shown below. Note that the package contains a Handset that should be set aside as a spare. If anything looks damaged, contact the inLighten Patient Support Program at 1-833-LIGHT-00 (1-833-544-4800).

The Lamira is made to be used with "AA" batteries or with the A/C Power Supply.
Using Batteries: Four (4) high quality "AA" batteries should provide 2 hours of total use.
Step D1: | Open the Battery Door on the Controller by placing your thumb on the tab of the Battery Door and firmly pulling the tab to open the Door (D-1).
Step D2: | Load the Batteries. Each Battery Chamber has a small figure that shows the proper position of each battery (D-2). Using the battery "tips" as guides and starting left-to-right for each row, insert the batteries: Tip Out, Tip In, Tip Out, Tip In. Close the Battery Door. To close the Battery Door, push it closed until you hear it "click" into place.
NOTE: | Rechargeable and Disposable Batteries have differences in storage life and output. If you plan to store the Controller for more than 30 days, it is recommended to remove the batteries to reduce the risk of battery leakage.
If you choose not to use the A/C Power Supply, you should have an extra battery set with you at all times.
Using the A/C Power Supply: The A/C Power Supply will automatically adjust to the incoming voltage and will power the Controller with or without installed batteries. It can be used worldwide, but requires "Plug Converters" for use outside the USA.
Step D3: | Plug the A/C Power Supply into the Controller. To connect the A/C Power Supply to the Controller, place the Controller on a clean, flat, stable surface. The plug inlet port is located on the underside of the gray Battery Door. Push the round end of the A/C Power Supply plug into the plug inlet port (D-3). Do not try to insert the A/C Power Supply into the front of the Controller.
Step D4: | Plug the A/C Power Supply into the wall outlet. Note that the A/C Power Supply will not charge the batteries in the Controller.

To reduce the risk of infection, illness, or injury from contamination or improper use, it is important to complete the following 2 steps:

1) Before first use, rinse and clean the Handset including the Aerosol Head. Moving forward, rinse and clean the Handset including the Aerosol Head right after each use (see Section F). Do not wash the Controller, Connection Cord, or A/C Power Supply. Use clear liquid soap made for washing dishes to clean the Handset. Do not use liquid dish soaps that are white or antibacterial liquid dish soaps because these may contain additives harmful to the Aerosol Head.
2) Before first use, disinfect the Handset including the Aerosol Head. Moving forward, disinfect the Handset including the Aerosol Head after every use (see Section G).

- Do not put the Handset or the Aerosol Head in the microwave oven.
- Do not try to clean the Handset or Aerosol Head in a dishwasher.
- Do not try to clean the Handset or the Aerosol Head with brushes or abrasives.

Handset Maintenance Summary (see the next page for complete instructions)
Instruction | When | Parts cleaned | Method | How Long | Comments
Wipe | After each use | - Medication Reservoir and Aerosol Chamber - Mouthpiece | Wipe with clean disposable paper towel. | 1 second per part | Wipe to remove residual medicine and then dispose of paper towel in trash with solid waste.
Rinse | Prior to first use, then after each use | - Aerosol Head - Medication Cap and Seal - Blue Valve - Medication Reservoir and Aerosol Chamber - Mouthpiece | Warm running tap water. | 10 seconds | Rinse each side of the Aerosol Head for 10 seconds.
Clean | Prior to first use, then after each use | - Aerosol Head - Medication Cap and Seal - Blue Valve - Medication Reservoir and Aerosol Chamber - Mouthpiece | Soak each piece in warm soapy water. While soaking swish or shake each piece. | 5 minutes | Use 3 to 5 drops of clear liquid dish soap in a bowl with enough warm water to cover all pieces. Soak longer if Handset has dried or if visibly dirty.
Rinse | Prior to first use, then after each use | - Aerosol Head - Medication Cap and Seal - Blue Valve - Medication Reservoir and Aerosol Chamber - Mouthpiece | Warm running tap water. | Until soap is removed. | Check each part and soak for another 5 minutes if any part looks dirty.
Disinfect | Prior to first use, then after each use | - Aerosol Head - Medication Cap and Seal - Blue Valve - Medication Reservoir and Aerosol Chamber - Mouthpiece | Boil in distilled water. | 5 minutes | Air-dry in a dust-free environment.

Your Handset including the Aerosol Head is not sterile. Contamination and moisture may cause the growth of bacteria and the Aerosol Head can be affected by ARIKAYCE left over in it. Before first use, it is important to rinse, clean, and disinfect your Handset including the Aerosol Head. Moving forward, rinse, clean, and disinfect the Handset including the Aerosol Head right after every use. If your Handset or Aerosol Head looks dirty, soak the parts in soapy water for longer than 5 minutes. Do not place the Handset or the Aerosol Head in a dishwasher.

Cleaning your Handset
 | Step F1: | Disconnect your Handset from the Connection Cord (F-1).
 | Step F2: | Remove the Medication Cap by turning counterclockwise and pulling straight up (F-2).
 | Step F3: | Remove the Mouthpiece from the Aerosol Chamber by pulling straight off (F-3). The Blue Flap must still be attached to the mouthpiece as shown in the picture.
 | Step F4: | Gently pull up on the tab to open the Handset and remove the Blue Valve (F-4).
 | Step F5: | Being careful to touch only the plastic outer ring of the Aerosol Head, press the 2 flexible plastic tabs on the side of the Aerosol Head towards each other and remove (F-5). After the Aerosol Head has been used 7 times, throw away (dispose of) and replace with a new one. Do not touch the center silver part of the Aerosol Head.
 | Step F6: | Gently wipe away any drops of medicine from the Medication Reservoir (F-6a), Aerosol Chamber (F-6b) and Mouthpiece (F-6c) before rinsing to reduce antibiotics added to water systems. Use only plain, dry paper towels or wipes. Do not use towels or wipes that have any chemicals added to them such as alcohol, lotion, or baby wipes. Be careful not to harm the parts. Do not wipe the Aerosol Head. Throw away paper towels by disposing in trash with solid waste.
 | Step F7: | Rinse each of the parts under warm running tap water for 10 seconds. Pay special attention to rinsing the Aerosol Head and rinse each side of the Aerosol Head for 10 seconds (F-7). Thorough rinsing of both sides of the Aerosol Head helps to prevent clogging and makes sure the Aerosol Head works properly. Never use a brush or any other object to clean the Aerosol Head.
 | Step F8: | Clean all Handset parts by adding a few drops of clear liquid dish soap and warm tap water to a clean tub or bowl. Cover the Handset parts in the warm soapy water and soak for 5 minutes, shaking them periodically (F-8).
 | Step F9: | Rinse all parts thoroughly under warm running tap water to remove soap (F-9). Check each part and soak for another 5 minutes if any of the parts look dirty. After all parts are cleaned and free from soap, disinfect your Handset.
 | Step F10: | Disinfect the Handset including the Aerosol Head after cleaning. In addition to cleaning ARIKAYCE from your Handset, you must also disinfect your Handset to remove bacteria and avoid infection. See Section G for instructions on how to disinfect your Lamira Handset.
Cleaning your Controller and Connection Cord
 | Step F11: | To reduce the risk of electric shock, disconnect all connections before cleaning. Switch off the Controller. Remove the Connection Cord and A/C Power Supply cord from the Controller.
 | Step F12: | Clean the Controller housing and Connection Cord as needed with a soft, clean, damp cloth. Do not place the Controller unit under water or allow liquid to get inside the Controller. Make sure moisture from the cloth does not enter the Controller.
Never let the Controller come in contact with water or cleaning agents. If liquid does get into the Controller, contact the inLighten Patient Support Program.

To prevent serious or fatal illness or injury caused by contamination, disinfect your Handset including the Aerosol Head after every use.
Step G1: | Clean your Handset right after every use with soapy water as described in Section F.
Step G2: | Disinfect your Handset after every use by boiling in distilled water. To disinfect with boiling water,; - Make sure the pot has enough distilled water to completely cover all the Handset parts including the Aerosol Head. - Heat the water to a boil in a clean pot. - Place the Handset parts, including the Aerosol Head into the boiling water. - Boil for a full 5 minutes. Note: It may be helpful to use a timer.
Step G3: | Air dry on a lint-free towel (G-3). After the parts are completely dry, wrap them in a lint-free towel for storage. Reassemble just before taking your next treatment. This is to make sure the Blue Valve will not become damaged.

Your Handset including the Aerosol Head is not sterile. Before first use, rinse, clean, and disinfect your Handset (See Section F). Moving forward, rinse, clean, and disinfect the Handset right after each use (See Section G). Inspect all parts to make sure they are cleaned and are not visibly damaged. Do not use dirty or damaged parts.
 |  |  | Clean and disinfect your Handset before the first use.
 | Step H1: | Clean and Disinfect your Handset before the first time you use it. See Sections F and G.
 | Step H2: | Wash your hands with soap and water and dry them well (H-2).
 | Step H3: | Open the Handset. The Medication Reservoir and the Aerosol Chamber are attached using a "hinge". First, gently pull up on the tab of the Medication Reservoir (H-3). This will release the Aerosol Chamber so that you may open it.
 | Step H4: | Insert the Blue Valve on top of the Aerosol Chamber (H-4). Make sure the 2 valve flaps are positioned down (valve flaps not bent) as shown in H-4a. Do not push the Blue Valve inside of the Aerosol Chamber. The Blue Valve should be placed on top of the Aerosol Chamber.
 | Step H5: | Insert the Aerosol Head Note: It is important that you do not touch the silver part of the Aerosol Head at any time during assembly. (H-5a)
 |  | Check to make sure the Aerosol Head is labeled "Lamira®". Do not use other eFlow Technology Aerosol Heads in the Lamira. (H-5b).
 |  | Carefully grasp the Aerosol Head by the 2 flexible plastic tabs on each side of the Aerosol Head. Turn the Aerosol Head so that "Lamira®" is facing toward you and is at the top of the Aerosol Head (H-5b).
 |  | Squeeze the two flexible plastic tabs together while inserting the metal arms and flexible plastic tabs into the Medication Reservoir (H-5c). You should feel the flexible plastic tabs "grab" as you insert it.
 | Step H6: | Close your Handset by pushing the Aerosol Chamber together with the Medication Reservoir until you hear a "snap" (no gaps along the blue valve edge) (H-6). If you do not hear a snap, open the Handset and check that the Blue Valve is seated properly (See Step H-4).
 | Step H7: | Attach Mouthpiece to your Handset. Make sure the Blue Flap is facing up (H-7) and is pressed in the slot on the Mouthpiece. Push the Mouthpiece straight onto the Handset. Make sure the Mouthpiece stays attached to the Handset during treatment.
 | Step H8: | Attach the Connection Cord by lining up the bottom of the Connector with the bottom of the Handset (H-8a) and pushing the Connection Cord upward against the rear underside of the Handset (H-8b) until you hear the parts snap together.
 | Step H9: | Connect the Connection Cord to the Controller. Push the round end of the Connection Cord into the plug inlet port located under the digital display (H-9). Place the Controller with the attached Handset on a clean, flat, stable surface.

Important information to know before you start; - If you use a bronchodilator (reliever), use the bronchodilator first, before using ARIKAYCE. Refer to your bronchodilator leaflet for information. The nebulizer for ARIKAYCE should only be used for giving ARIKAYCE. - Each vial of ARIKAYCE is for single (1 time) use only. - Do not use ARIKAYCE with any other type of Handset or Aerosol Head than the one provided in the carton. - Do not put other medicines in the Lamira Nebulizer Handset. - Do not drink the liquid in the vial. - Do not use ARIKAYCE if the expiration date has passed.; Getting your ARIKAYCE ready before adding it to the Lamira Nebulizer Handset. |  | Your ARIKAYCE should be at room temperature before use to make sure that your Lamira operates properly. Bring ARIKAYCE to room temperature by removing it from the refrigerator at least 45 minutes before use. Do not use if your ARIKAYCE has been frozen. Do not use other medicine in your Handset.
Step I1: | Shake the ARIKAYCE vial well for a minimum of 10 to 15 seconds, AND UNTIL THE MEDICINE LOOKS THE SAME THROUGHOUT AND WELL MIXED (I-1).
Step I2: | Lift orange cap from vial and throw away (dispose of) the orange cap (I-2).
Step I3: | Grip metal ring on top of the vial. Pull it down gently (I-3) until 1 side breaks away from the vial but do not pull the tab completely off (I-3a).
Step I4: | Pull the metal band from around the vial top in a circular motion until it comes off completely from the vial (I-4). Throw away (dispose of) the metal band after it is removed.
Step I5: | Carefully remove the rubber stopper by pulling it upward (I-5).
Step I6: | Make sure your Handset is placed on a clean, flat, stable surface. Pour 1 vial of ARIKAYCE into the Medication Reservoir (I-6). Do not use more than 1 vial for each treatment.
Step I7: | Attach the Medication Cap by lining up the Tabs on the Medication Cap with the Tab Slots on the Medication Reservoir (I-7). Turn the Medication Cap clockwise until it stops. As the Medication Cap is turned, the inner cap of the Medication Cap should rise.
Step I8: | To begin your treatment, sit in a relaxed, upright position. Press and hold the On/Off (2 to 3 seconds) (I-8) until the start screen appears on the LCD display (I-8a). You will also hear 1 "beep" and the status light will turn green. The Lamira is now On. After treatment begins, the treatment screen (I 8b) will replace the start screen (I-8a) and aerosol mist will begin to flow.
Step I9: | Insert the Mouthpiece by placing it on top of your bottom lip and tongue. Close your lips around the Mouthpiece but do not cover the blue flap (I-9). Take slow, deep breaths then breathe normally in and out through the Mouthpiece until your treatment is complete. Your treatment should take about 14 minutes, but could take up to 20 minutes.
 | Hold the Handset level throughout your treatment. If the Handset is held at an angle over 45 degrees (I-9a), it will sound 2 beeps (and LED flashes) and shut off after 30 seconds. If this occurs, hold the Handset level and press the On/Off Button to start your treatment again.
Note: | The Lamira can be paused at any time during operation by pressing the On/Off button for 1 second. The screen will go from On (I-9b) to Pause (I-9c), a 5-beep alarm tone will sound, and the status light on the Controller will flash. To resume your treatment, press the Controller On/Off button for 1 full second. The Controller will run for up to 20 minutes. If your treatment is not complete after 20 minutes, press the On/Off button to continue treatment.
Important Information: The amount of time to nebulize your ARIKAYCE may change from dose to dose and may become longer unless the cleaning and maintenance instructions are followed (See Maintaining Your Lamira).
Step I10: | At the end of your treatment, the following will happen:; - The Lamira will beep 2 times. - The Dose Complete Checkmark will appear briefly on the screen (I-10a). - The Controller will automatically shut off.
 | Always check the Medication Reservoir by removing the Medication Cap (I-10b) to make sure you have completed your dose. If more than a few drops of ARIKAYCE remains, replace the Medication Cap (I-10c) and press On/Off start button and complete your dose. Change your Aerosol Head after 7 uses. After the Aerosol Head has been used 7 times, replace it with a new Aerosol Head during the cleaning process. Follow the instructions in Steps F6 through F9 and replace the Aerosol Head with a new one. Change your Handset after 28 days. After the Handset has been used for 28 days, replace it with a new Handset during the cleaning process. | Important: Clean and disinfect your Handset after each use. See sections F and G for instructions. Change your Aerosol Head after 7 uses. Lamira Handset is to be used for 28 days.

QUESTION 1: How long should my ARIKAYCE treatment take?

Answer: With normal operation and proper cleaning, your Handset should deliver 1 vial of ARIKAYCE in about 14 minutes but could take up to 20 minutes. Your Lamira should automatically shut off shortly after your treatment is complete or after 20 minutes. If the Lamira turns off after 20 minutes, check the Medication Reservoir. If it is empty, you have received your full dose.

QUESTION 2: How much ARIKAYCE should be left in the Medication Reservoir at the end of my treatment?

Answer: Only a drop of ARIKAYCE should remain in the Medication Reservoir. If more than a drop remains, start the Controller and complete your dose. Then clean the Aerosol Head (Section F). If after proper cleaning, more than a drop remains in the Medication Reservoir, contact the inLighten Patient Support Program at 1-833-LIGHT-00 (1-833-544-4800).

QUESTION 3: When I turn on my Nebulizer, nothing happens. There does not seem to be any power.

Answer: If you are using batteries, use the figures in each Battery Compartment to check that the batteries are inserted correctly. If the batteries are positioned properly, check to see if the light is blinking on the Controller signaling low battery power. If it is, replace the batteries or use the A/C Power Supply.
  Answer: If you are using the A/C Power Supply, check the connection to be sure it is firmly connected to the Power Supply Port located underneath the Battery Compartment.
  Be sure that the A/C Power Supply is plugged into a working wall outlet.

QUESTION 4: Sometimes I have trouble removing the Medication Cap at the end of my therapy session.

Answer: A vacuum has formed in the Medication Reservoir. Remove the Connection Cord, open the Handset and carefully remove the Aerosol Head. The Medication Cap will then be easier to remove.

QUESTION 5: What if no mist is coming out of your Handset?

Answer: First, make sure ARIKAYCE is at room temperature before use. If ARIKAYCE is not at room temperature, your nebulizer may not mist immediately. Secondly, check that the Controller has power and is not paused. Thirdly, make sure the Connection Cord is correctly attached. Fourthly, check to be sure that your Handset has been assembled properly (Section H) and that the Handset is level throughout your treatment. Lastly, check to be sure that the ARIKAYCE is in the Medication Reservoir. If you are still having a problem, contact inLighten Patient Support Program at 1-833-LIGHT-00 (1-833-544-4800).

QUESTION 6: What if liquid is leaking from my Handset during my treatment?

Answer: To prevent leaks, be sure (1) the Blue Valve is properly attached to the Aerosol Chamber (valve flaps not bent) (Fig H-4a), (2) the Aerosol Head is inserted correctly, (3) the Medication Cap is screwed on fully, and (4) the Medication Reservoir and Aerosol Chamber are closed properly and snapped together (no gaps along the blue valve edge)(H-6).
  Answer: It is normal to have some liquid collect in the Aerosol Chamber and some liquid may leak from the mouthpiece. Try to hold the Handset level so that liquid does not pour out of the Mouthpiece.

QUESTION 7: What if my Controller shuts off before my treatment begins, or does not restart?

Answer: Low voltage. Replace the batteries or use the A/C Power Supply. Press the On/Off button to continue your treatment.
  Answer: Your Handset was tilted above 45°. Hold your Handset level and press the On/Off button to continue your treatment.
  Answer: ARIKAYCE is cold. Allow the ARIKAYCE to warm to room temperature and then press the On/Off button to continue your treatment.
  Answer: Lost power while using the A/C Power Supply. It is recommended to keep batteries inserted in the device as backup in case power is interrupted while using the A/C Power Supply. Doing so can help avoid treatment disruption.

QUESTION 8: What if my Controller does not shut off at the end of my treatment?

Answer: Your Controller may take up to 60 seconds to shut off after you complete your dose. If you wish to stop your Controller earlier, press the On/Off button.
  Answer: Disconnect the A/C Power Supply from the Controller and remove the batteries. Then, reinsert the Batteries following the procedure in Section D.
  Answer: If this situation continues 3 or 4 times, contact the inLighten Patient Support Program at 1-833-LIGHT-00 (1-833-544-4800).

QUESTION 9: How long will a new set of batteries last?

Answer: A new set of batteries should provide 2 hours of total use.
  Answer: Consider using rechargeable batteries.

QUESTION 10: What if something arrives damaged?

Answer: Contact the inLighten Patient Support Program at 1-833-LIGHT-00 (1-833-544-4800).

 | Fault and Condition |  | Possible Cause and Solution
1 | Steady |  | Controller running on A/C Power.
2 | Steady |  | Controller running on battery power.
3 | Flashing |  | Empty battery, replace batteries or switch to A/C power.
4 | Flashing |  | Low battery, replace batteries or switch to A/C power.
 | The LED flashes and the battery symbol is blinking during treatment
5 | Flashing |  | Bad or missing Connection Cord. Check Connection Cord between Handset and Controller. Bad or missing Aerosol Head. Correct then restart Controller.
 | Lamira turns on but the LED flashes and the LCD display flashes this symbol
6 | Flashing |  | No ARIKAYCE detected. Add ARIKAYCE. If you have already added ARIKAYCE, gently tap the Handset, hold the Handset level and restart the Controller.
 | Lamira beeps 1x, then beeps high-low with the LED flashing and the LCD display flashing this symbol
7 | Flashing |  | Have reached 20 minute maximum time and will shut down. If ARIKAYCE remains, restart the Controller. After treatment is complete, clean and disinfect the Handset including the Aerosol Head.
 | Lamira beeps low-high 3 times, the LED flashes, the LCD displays this symbol and then turns off
8 | Steady |  | Misting and working properly.
 | Lamira beeps 1 time and LCD shows this symbol
9 | Steady |  | Controller has paused. To resume press On/Off button.
10 | Flashing |  | Press button to start treatment.
11 | Brief |  | Functioning properly, the Controller has started properly.
12 | Brief |  | No ARIKAYCE remaining, your treatment is done. If ARIKAYCE is remaining, your Handset might be tilted. Keep Handset level, gently tap Handset and restart Controller.
 | The Lamira beeps 2 times, displays this checkmark symbol, then turns off.
13 | The Lamira cannot be activated and no green LED, no screen, and no beep. |  | Bad, missing or misloaded batteries. Bad or missing A/C Power Supply.
14 | The Lamira beeps 1 time and begins to produce a mist, then stops and shuts off with no beep, no LED, and with ARIKAYCE still present. |  | Bad batteries or bad A/C Power Supply. Replace batteries or A/C Power Supply and restart Controller.
15 | The Lamira stops before ARIKAYCE is completely used up. |  | Lost power. Replace batteries or use A/C Power Supply. Tilted Handset. Keep Handset level, gently tap Handset and restart Controller. Lost power while using the A/C Power Supply. It is recommended to keep batteries inserted in the device as backup in case power is interrupted while using the A/C Power Supply. Doing so can help avoid treatment disruptions.
16 | The Lamira does not stop automatically after all ARIKAYCE is consumed. |  | Clean and disinfect the Aerosol Head. If condition continues, contact the inLighten Patient Support Program at 1-833-LIGHT-00 (1-833-544-4800).
17 | Longer than normal nebulization time. |  | Aerosol Head is dirty. Clean and disinfect the Aerosol Head. Replace the Aerosol Head with a new one from your kit after 7 uses.
18 | Handset leaks. |  | Make sure Blue Valve is placed correctly in the Handset and the 2 flaps point into the Handset Chamber (see Section H). Make sure Aerosol Head is correctly placed in the Handset. It is normal to have some liquid collect in the Aerosol Chamber and Mouthpiece. The amount depends on the volume of the ARIKAYCE and on your breathing pattern.
19 |  |  | The On button was accidently pressed for 10 seconds, which activated the easycare function. The easycare is an accessory that assists in cleaning the Aerosol Head but it is not used for your Lamira. Press the On button briefly to turn-off the Controller and stop the easycare function.

Mechanical
Weight: Controller and Handset | approx. 8.2 oz.
Weight: Controller, Handset, and Batteries | approx. 11 oz.
Handset Dimensions (W × H × D) | 2.0" × 2.4" × 5.5"
Controller Dimensions (H × Ø) | 1.6" × 4.6"
Minimum Fill Volume | 0.5 mL
Maximum Fill Volume | 8.4 mL

Electrical
Electrical Requirements | 110 V - 240 V, 50 Hz/60 Hz
Power Wattage | 2.0 Watts under normal load

Transport and Storage
Temperature | -13° to 158° F
Relative Humidity (non-condensing) | 0% to 93%
Air Pressure | 9 to 15 PSI

Operational
Temperature | 41° to 104° F
Relative Humidity (non-condensing) | 15% to 93%
Air Pressure | 10 to 15 PSI

Device Classification According to IEC 60601-1
Type of electric shock protection (A/C Power Supply) | Protection Class II
Degree of protection from electric shock of part used (nebulizer) | Type BF
Degree of protection against water ingress per IEC 60529 IP rating (controller) | IP 22
Degree of protection when in the presence of flammable mixtures | No protection
Continuous operation | Operating mode

Device Performance Characteristics

 | Mean | Range [Range - two-sided tolerance interval, proportion of total population=0.95]
Total Delivered Dose by Breath Simulation [Breath simulation - tidal volume of 500 mL, 15 breath per minutes, and inhalation:exhalation ratio is 50:50] (mg) | 312.1 | 273.8 – 350.4
Total Delivered Dose by Breath Simulation (% of label claim [label claim - 590 mg]) | 52.9 | 46.4 – 59.4
MMAD [MMAD - Mass Median Aerodynamic Diameter] by NGI [NGI - Next Generation Impactor] (µm) | 4.45 | 4.38 – 4.52
GSD [GSD - Geometric Standard Deviation] | 1.59 | 1.59 – 1.60
Respiratory Dose by NGI (≤ 5µm, mg) | 327.1 | 316.5 – 337.6
Respiratory Fraction by NGI (≤5µm, % of delivered dose) | 55.6 | 53.8 – 57.4

Handset materials

Polypropylene, polyamide, silicone, stainless steel, thermoplastic elastomers. Does not contain any natural rubber (latex).

Disposal

The Lamira components and batteries must be disposed of in accordance with local (state, county or municipal) regulations.

Manufactured by:

PARI Respiratory Equipment, Inc.
2412 PARI Way
Midlothian, Virginia 23112 USA
For patent information: www.PARI.com/ip

©2018 PARI Pharma GmbH. All rights reserved. The PARI logo is a registered trademark of PARI GmbH. Lamira®, Altera®, eRapid®, and eFlow® logo are registered trademarks of PARI Pharma GmbH. Insmed®, ARIKAYCE®, and inLighten™ are trademarks of Insmed Incorporated.

This Instructions for Use has been approved by the U.S. Food and Drug Administration

678D0204
Rev D 01/25

PRINCIPAL DISPLAY PANEL - 8.4 mL Vial Carton

1-833-LIGHT-00
(1-833-544-4800)

Contains 28 sterile unit-dose vials
Each vial contains amikacin 590 mg/8.4 mL
(equivalent to amikacin sulfate 788 mg/8.4 mL)

For oral inhalation only

ARIKAYCE®
(amikacin liposome
inhalation suspension)
590 mg/8.4 mL vials

Limited Population*

insmed®

Attention Patients:
Store refrigerated until expiration date on vial. Do not freeze. Once expired,
discard any unused medicine. ARIKAYCE can be stored at room temperature
up to 25°C (77°F) for up to 4 weeks. Once at room temperature, any unused
medicine must be discarded at the end of 4 weeks.

*See the full prescribing information for ARIKAYCE
for information about the limited population

ARIKAYCE.COM